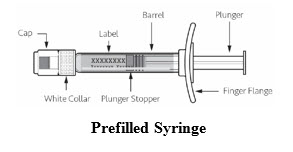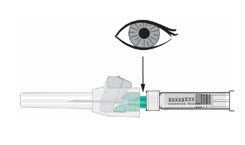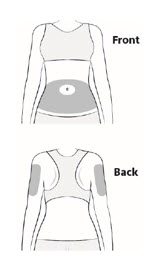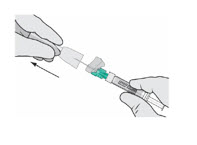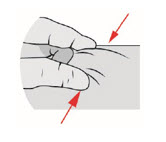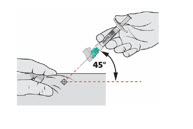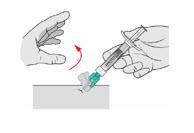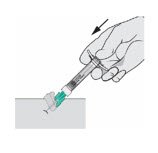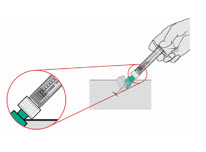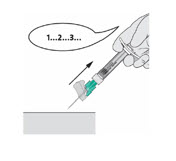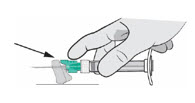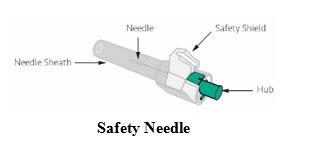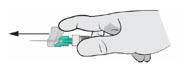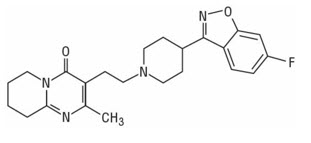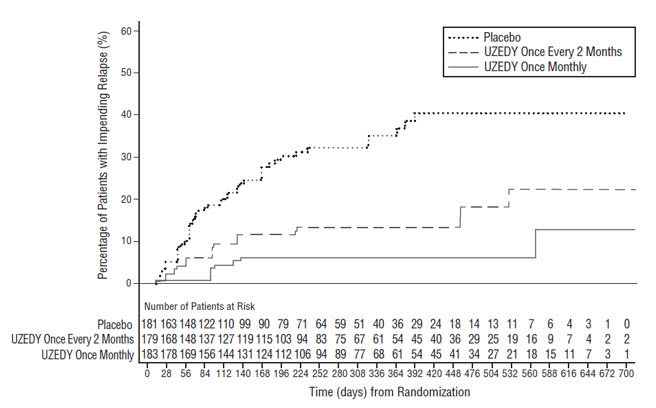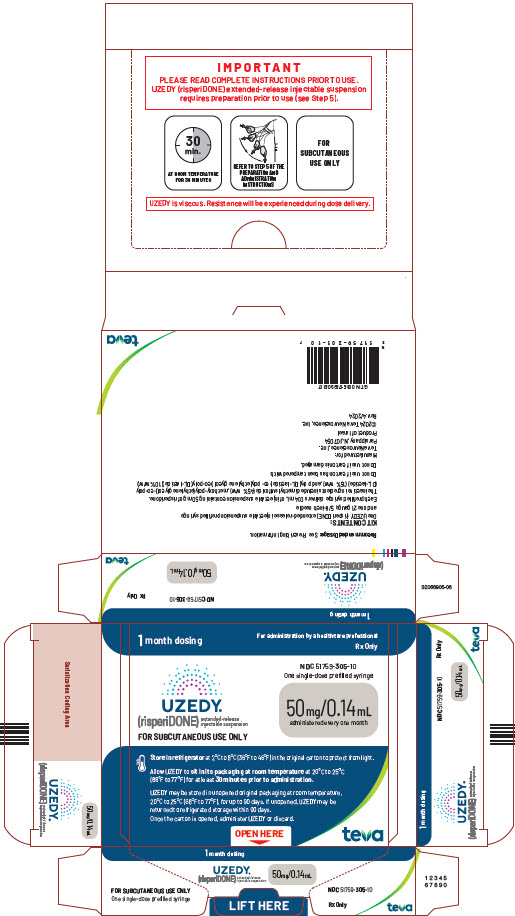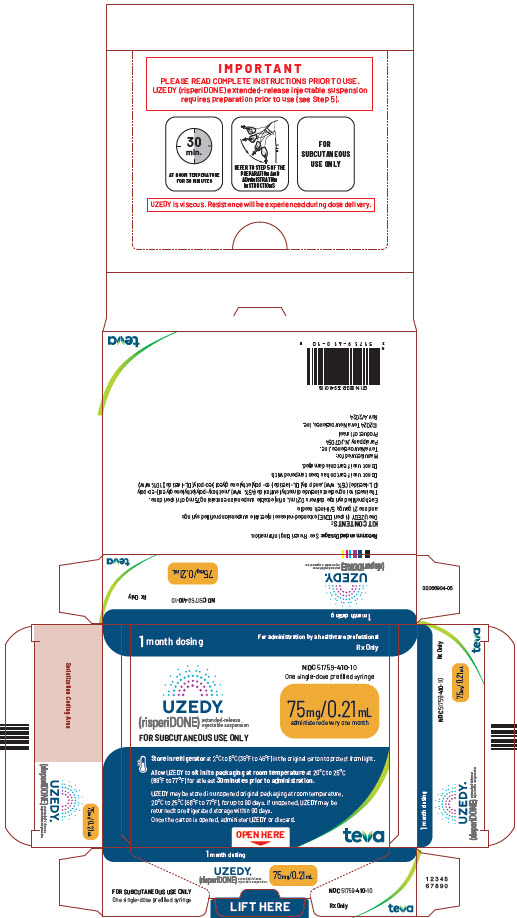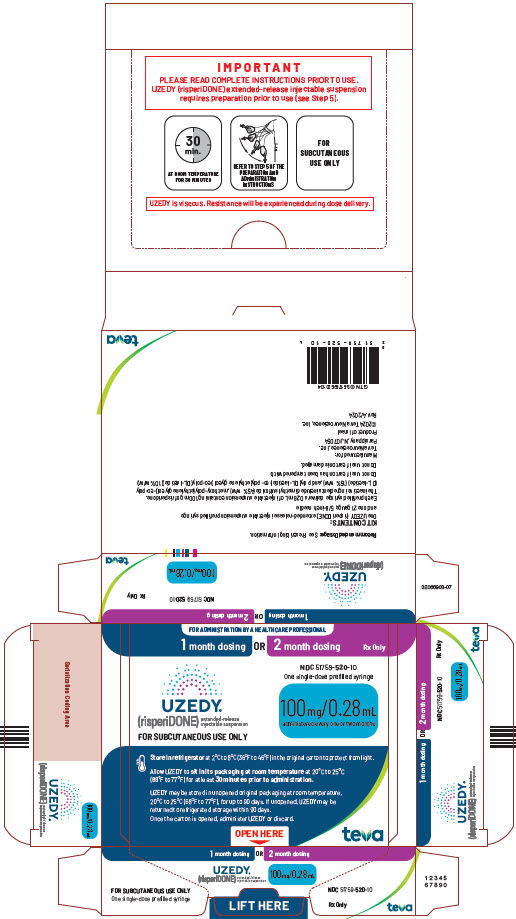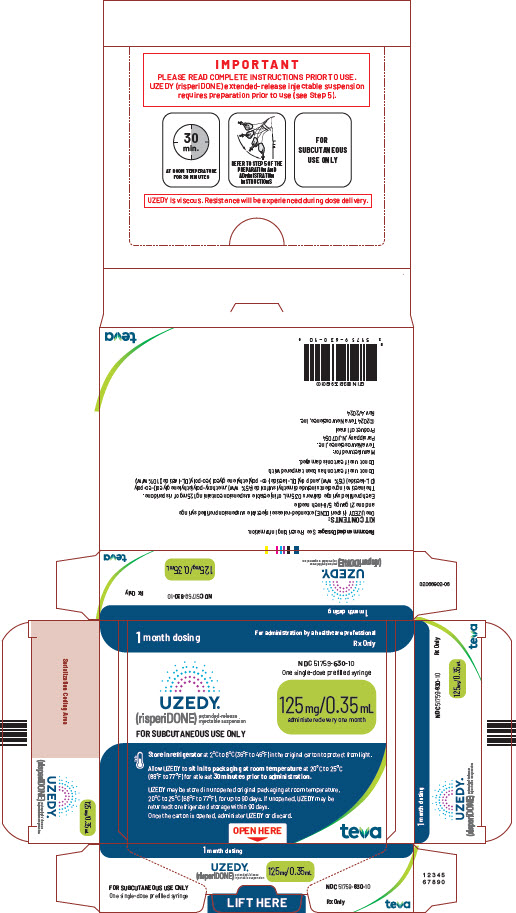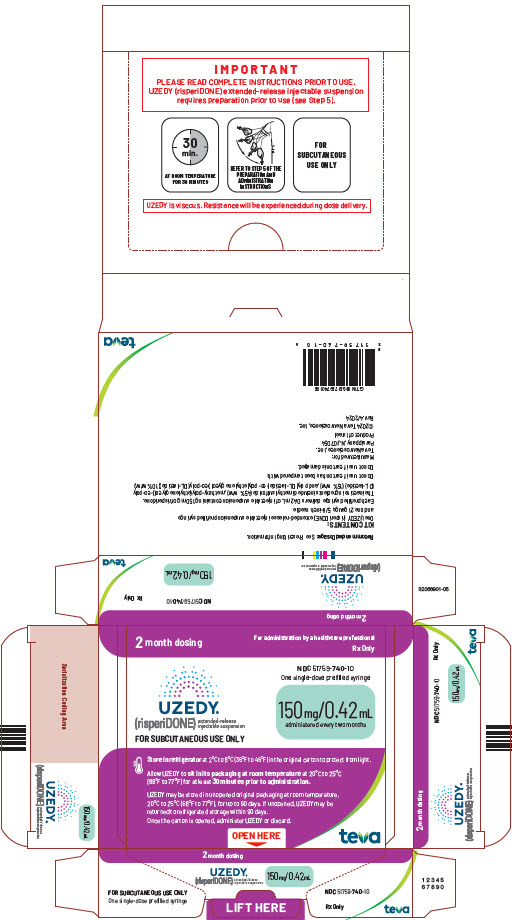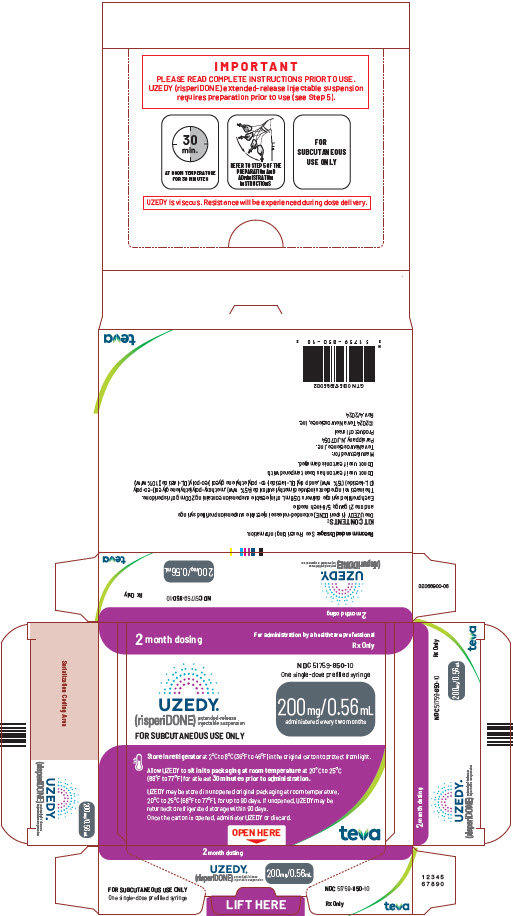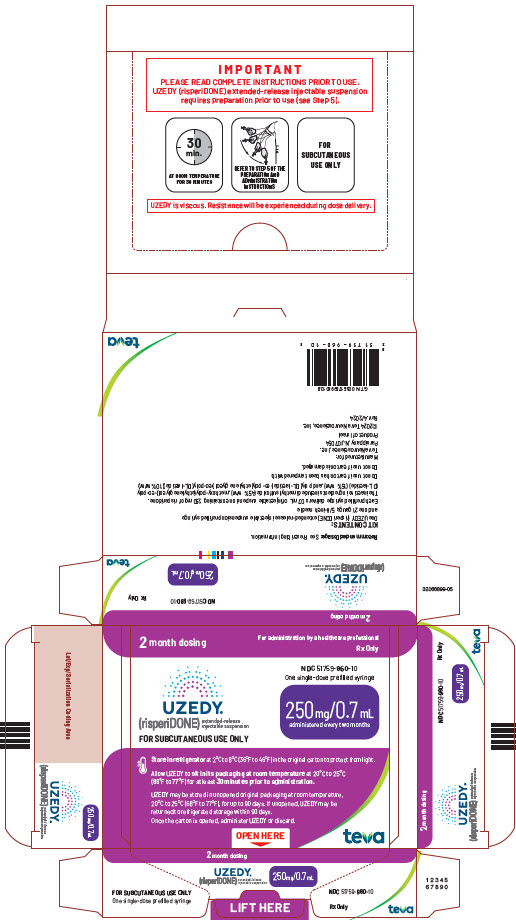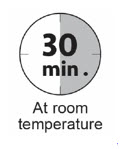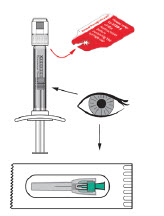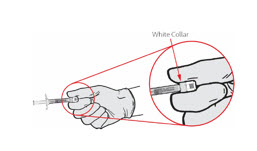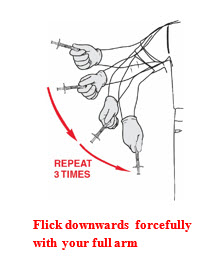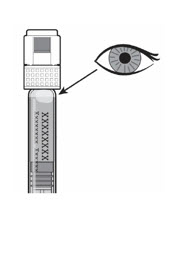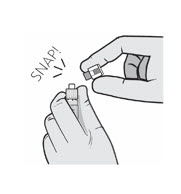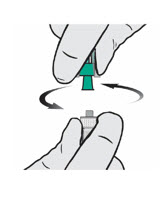 DRUG LABEL: UZEDY
NDC: 51759-305 | Form: INJECTION, SUSPENSION, EXTENDED RELEASE
Manufacturer: Teva Pharmaceuticals USA, Inc.
Category: prescription | Type: HUMAN PRESCRIPTION DRUG LABEL
Date: 20251009

ACTIVE INGREDIENTS: RISPERIDONE 50 mg/0.14 mL
INACTIVE INGREDIENTS: DIMETHYL SULFOXIDE

HIGHLIGHTS OF PRESCRIBING INFORMATION

These highlights do not include all the information needed to use UZEDY® safely and effectively. See full prescribing information for UZEDY.
UZEDY (risperidone) extended-release injectable suspension, for subcutaneous use
Initial U.S. Approval: 1993

RECENT MAJOR CHANGES

Indications and Usage (1.1, 1.2) 10/2025
Dosage and Administration (2.1, 2.2, 2.3) 10/2025
Warnings and Precautions (5.6) 1/2025

WARNING: INCREASED MORTALITY IN ELDERLY PATIENTS WITH DEMENTIA-RELATED PSYCHOSIS

See full prescribing information for complete boxed warning.

Elderly patients with dementia-related psychosis treated with antipsychotic drugs are at an increased risk of death. UZEDY is not approved for use in patients with dementia-related psychosis. (5.1)

1 INDICATIONS AND USAGE

UZEDY is an atypical antipsychotic indicated:

- for the treatment of schizophrenia in adults. (1.1)
- as monotherapy or as adjunctive therapy to lithium or valproate for the maintenance treatment of bipolar I disorder in adults. (1.2)

2 DOSAGE AND ADMINISTRATION

- Establish tolerability with oral risperidone prior to initiating UZEDY. (2.1)
- Administer UZEDY by subcutaneous injection in the abdomen or upper arm by a healthcare professional. Do not administer by any other route. (2.1)
- See Full Prescribing Information for important preparation and administration information. (2.7)

Schizophrenia

- Initiate UZEDY at the clinically appropriate dose using the following table. (2.2)

Comparable Daily Oral Risperidone Therapy | UZEDY Dosage Once Monthly | UZEDY Dosage Once Every 2 Months
2 mg | 50 mg | 100 mg
3 mg | 75 mg | 150 mg
4 mg | 100 mg | 200 mg
5 mg | 125 mg | 250 mg

Bipolar I disorder

- Following establishment of tolerability with oral risperidone, initiate UZEDY at the clinically appropriate dose using the following table. (2.3)

Comparable Daily Oral Risperidone Therapy | UZEDY Dosage Once Monthly
2 mg | 50 mg
3 mg | 75 mg
4 mg | 100 mg

- For patients currently receiving risperidone long acting intramuscular injectable given once every 2 weeks, switch to UZEDY as a once monthly injection, starting at least 5 weeks after the last dose of risperidone long acting injectable given once every 2 weeks. (2.3)
- Switch to UZEDY at the clinically appropriate dose using the following table. (2.3).

Another Risperidone Long-Acting Intramuscular Injection Given Once Every 2 Weeks | UZEDY Dosage Once Monthly
25 mg | 50 mg
37.5 mg | 75 mg
50 mg | 100 mg

3 DOSAGE FORMS AND STRENGTHS

Extended-release injectable suspension, in the strengths of risperidone: 50 mg/0.14 mL, 75 mg/0.21 mL, 100 mg/0.28 mL, 125 mg/0.35 mL, 150 mg/0.42 mL, 200 mg/0.56 mL, and 250 mg/0.7 mL single-dose prefilled syringes. (3)

4 CONTRAINDICATIONS

Known hypersensitivity to risperidone, paliperidone, or to any of the components in UZEDY. (4)

5 WARNINGS AND PRECAUTIONS

- Cerebrovascular Adverse Reactions, in Elderly Patients with Dementia-Related Psychosis: Increased incidence of cerebrovascular reactions (e.g., stroke, transient ischemia attack). (5.2)
- Neuroleptic Malignant Syndrome (NMS): Manage with immediate discontinuation and close monitoring. (5.3)
- Tardive Dyskinesia: Discontinue treatment if clinically appropriate. (5.4)
- Metabolic Changes: Monitor for hyperglycemia/diabetes mellitus, dyslipidemia, and weight gain. (5.5)
- Hyperprolactinemia: Prolactin elevations occur and persist during chronic administration. Long-standing hyperprolactinemia, when associated with hypogonadism, can lead to decreased bone density in females and males. (5.6)
- Orthostatic Hypotension and Syncope: Monitor heart rate and blood pressure and warn patients with known cardiovascular disease or cerebrovascular disease, and risk of dehydration or syncope. (5.7)
- Leukopenia, Neutropenia, and Agranulocytosis: Perform complete blood counts (CBC) in patients with a history of clinically significant low white blood cell count (WBC) or history of leukopenia or neutropenia. Consider discontinuing UZEDY if a clinically significant decline in WBC occurs in the absence of other causative factors. (5.9)
- Potential for Cognitive and Motor Impairment: Use caution when operating machinery. (5.10)
- Seizures: Use cautiously in patients with a history of seizures or with conditions that lower the seizure threshold. (5.11)
- Priapism: Priapism has been reported. Severe priapism may require surgical intervention. (5.13)

6 ADVERSE REACTIONS

The most common adverse reactions with risperidone in patients with schizophrenia (≥5% and greater than placebo) were parkinsonism, akathisia, dystonia, tremor, sedation, dizziness, anxiety, blurred vision, nausea, vomiting, upper abdominal pain, stomach discomfort, dyspepsia, diarrhea, salivary hypersecretion, constipation, dry mouth, increased appetite, increased weight, fatigue, rash, nasal congestion, upper respiratory tract infection, nasopharyngitis, and pharyngolaryngeal pain. (6.1)

The most common adverse reactions with risperidone in patients with bipolar disorder were weight increased (5% in monotherapy trial) and tremor and parkinsonism (≥10% in adjunctive therapy trial). (6.1)

The most common injection site reactions with UZEDY in patients with schizophrenia (≥5% and greater than placebo) were pruritus and nodule. (6.1)

To report SUSPECTED ADVERSE REACTIONS, contact Teva Pharmaceuticals at 1-888-483-8279 or FDA at 1-800-FDA-1088 or www.fda.gov/medwatch.

7 DRUG INTERACTIONS

- Strong CYP2D6 inhibitors (e.g., fluoxetine, paroxetine): Increase risperidone plasma concentration. (2.6, 7.1)
- Strong CYP3A4 inducers (e.g., carbamazepine): Decrease plasma concentrations of risperidone. (2.6, 7.1)

8 USE IN SPECIFIC POPULATIONS

Pregnancy: May cause extrapyramidal and/or withdrawal symptoms in neonates with third trimester exposure. (8.1)

FULL PRESCRIBING INFORMATION

WARNING: INCREASED MORTALITY IN ELDERLY PATIENTS WITH DEMENTIA-RELATED PSYCHOSIS

Elderly patients with dementia-related psychosis treated with antipsychotic drugs are at an increased risk of death. UZEDY is not approved for the treatment of patients with dementia-related psychosis and has not been studied in this patient population [see Warnings and Precautions (5.1)].

1 INDICATIONS AND USAGE

1.1 Schizophrenia

UZEDY is indicated for the treatment of schizophrenia in adults.

1.2 Bipolar Disorder

UZEDY is indicated as monotherapy or as adjunctive therapy to lithium or valproate for the maintenance treatment of Bipolar I Disorder in adults.

2 DOSAGE AND ADMINISTRATION

2.1 General Administration Information

For patients who have never taken risperidone, establish tolerability with oral risperidone prior to initiating UZEDY.

UZEDY must be administered by a healthcare professional as an abdominal or upper arm subcutaneous injection. Do not administer UZEDY by any other route.

For detailed preparation and administration instructions, see Dosage and Administration (2.7).

2.2 Dosage Recommendations for the Treatment of Schizophrenia

To start UZEDY for the treatment of schizophrenia, switch from oral daily risperidone. Initiate UZEDY, as either a once monthly injection or a once every 2 month injection, the day after the last dose of oral therapy. See Table 1 to determine how to switch from oral risperidone to UZEDY once monthly (50 mg, 75 mg, 100 mg, or 125 mg) or once every 2 months (100 mg, 150 mg, 200 mg, or 250 mg) given via abdominal or upper arm subcutaneous injection. Neither a loading dose nor supplemental oral risperidone doses are recommended when switching.

Table 1: Dosage Recommendations for Switching from Daily Oral Risperidone to UZEDY Given Once Monthly or Once Every 2 Months
Comparable Daily Oral Risperidone Therapy | UZEDY Dosage Once Monthly | UZEDY Dosage Once Every 2 Months
2 mg | 50 mg | 100 mg
3 mg | 75 mg | 150 mg
4 mg | 100 mg | 200 mg
5 mg | 125 mg | 250 mg

Patients can switch between doses of UZEDY once monthly and once every 2 months by administering the first dose of the new dosing regimen on the next scheduled date of administration in the original dosing regimen. Revise the dose administration schedule to reflect the change.

2.3 Dosage Recommendations for Maintenance Treatment of Bipolar I Disorder

Following establishment of tolerability with oral risperidone, start UZEDY as a once monthly injection for monotherapy or adjunctive therapy to lithium or valproate for the maintenance treatment of bipolar I disorder, according to the dosage recommendations in Table 2. UZEDY once every 2 months injection is not recommended for the maintenance treatment of bipolar I disorder.

Table 2: Dosage Recommendations for Switching from Daily Oral Risperidone to UZEDY Given Once Monthly
Comparable Daily Oral Risperidone Therapy | UZEDY Dosage Once Monthly
2 mg | 50 mg
3 mg | 75 mg
4 mg | 100 mg

For patients currently receiving risperidone long acting intramuscular injectable given once every 2 weeks, switch to UZEDY as a once monthly subcutaneous injection, starting at least 5 weeks after the last dose of risperidone long acting intramuscular injectable given once every 2 weeks. Refer to Table 3 to determine how to switch from risperidone long acting injectable given once every 2 weeks to UZEDY once monthly (50 mg, 75 mg, 100 mg) subcutaneous injection given via abdominal or upper arm. Neither a loading dose nor supplemental oral risperidone doses are recommended when initiating UZEDY.

Table 3: Dosage Recommendations for Switching From Another Risperidone Long-Acting Intramuscular Injection Given Once Every 2 Weeks To UZEDY Given Once Monthly
Another Risperidone Long-Acting Intramuscular Injection Given Once Every 2 Weeks | UZEDY Dosage Once Monthly
25 mg | 50 mg
37.5 mg | 75 mg
50 mg | 100 mg

2.4 Missed Doses

When a dose of UZEDY is missed, administer the next UZEDY injection as soon as possible. Do not administer more frequently than recommended.

2.5 Dosage Modifications in Patients with Renal Impairment or Hepatic Impairment

Prior to initiating UZEDY in patients with renal or hepatic impairment, titrate with oral risperidone to at least 2 mg once daily. Following oral titration, and based on clinical response and tolerability, the recommended dosage of UZEDY is 50 mg once monthly [see Use in Specific Populations (8.6, 8.7) and Clinical Pharmacology (12.3)].

2.6 Dosage Modifications for Concomitant Use with Strong CYP2D6 Inhibitors and Strong CYP3A4 Inducers

Concomitant Use with Strong CYP2D6 Inhibitors

When initiation of fluoxetine or paroxetine is considered, place patients on a lower dose of UZEDY prior to the planned start of fluoxetine or paroxetine therapy to adjust for the expected increase in plasma concentrations of risperidone.

When fluoxetine or paroxetine is initiated in patients receiving the recommended dose of 50 mg once monthly or 100 mg once every 2 months of UZEDY, continue treatment with these doses unless clinical judgment necessitates interruption of UZEDY [see Drug Interactions (7.1)].

Concomitant Use with Strong CYP3A4 Inducers

At the initiation of therapy with strong CYP3A4 inducers (such as carbamazepine), patients should be closely monitored during the first 4 to 8 weeks since the dose of UZEDY may need to be adjusted. A dose increase, or additional oral risperidone, may be considered.

On discontinuation of a strong CYP3A4 inducer, re-evaluated the dosage of UZEDY or any additional oral risperidone therapy and, if necessary, decrease to adjust for the expected increase in plasma concentration of risperidone.

On discontinuation of a strong CYP3A4 inducer in a patient treated with UZEDY 50 mg once monthly or 100 mg once every 2 months, continue treatment with these doses unless clinical judgment necessitates interruption of UZEDY [see Drug Interactions (7.1)].

2.7 Preparation and Administration Instructions

- Read the instructions for preparation and administration below before administering UZEDY.
- For subcutaneous injection only. Do not inject by any other route.
- To be administered by a healthcare professional only.
- Allow UZEDY to come to room temperature for at least 30 minutes prior to administration.
- As a universal precaution, always wear gloves.

STEP 1

Check to make sure UZEDY kit contains:

- One sterile single-dose, prefilled glass syringe
- One sterile 21G x 5/8” needle

Do not substitute any components of the kit for administration.

STEP 2

Remove the kit from refrigerated storage and allow the package to sit at room temperature (20°C to 25°C [68°F to 77°F]) for at least 30 minutes.

Note: UZEDY is a solid at refrigerated temperatures and must reach room temperature prior to administration. Do not warm any other way and keep protected from light.

STEP 3

Check that the drug in the syringe is white to off-white, opaque in color, and free from non-white particulate matter. Check that the pouch label states the needle size is 21G x 5/8”.

Do not use if any component of the kit is damaged or if the expiration date has passed.

STEP 4

Expose the safety needle hub by peeling back the paper tab of the needle pouch. Set aside for use in Step 7.

STEP 5

IMPORTANT: This step must be performed to ensure complete dosing. UZEDY is viscous and forceful downward flicks are required to move the bubble to the cap of the syringe. Failure to move the bubble to the cap of the syringe could result in incomplete dosage.

Firmly hold the syringe by the white collar.

Flick Syringe Forcefully Three Times to Move the Bubble to the Cap

- Flick with a forceful downward whipping motion of your full arm to move the bubble to the cap of the syringe.
- Repeat this action 3 times to ensure that the bubble is at the cap of the syringe.

Note: Standing while you do this may help achieve required force.

Check that the Bubble is at the Cap of the Syringe

- The bubble will appear partially opaque.
- Holding the syringe up to light or against a dark backdrop may improve visibility.
- If the bubble is not at the cap, repeat Step 5 until it is.

STEP 6

Hold the syringe vertically by the white collar. Bend and snap off the cap.

Do not touch the syringe tip to avoid contamination.

STEP 7

Attach the Needle to the Syringe

- Hold the syringe vertically with the white collar at the top.
- Push the green hub of safety needle inside the white collar of syringe and rotate the safety needle while holding the white collar until secure and tight.

Inspect the needle connection to check that the hub is not damaged.

STEP 8

Select Injection Site from the Following Areas:

- Stomach area (abdomen) around the belly button
- Back and outer area of the upper arms

Do not inject UZEDY anywhere except in the areas specified above.

Do not inject UZEDY into an area that is tender, red, bruised, callused, tattooed, hard, or has scars or stretch marks.

STEP 9

Clean the Injection Site with an alcohol wipe.

STEP 10

Remove the needle sheath by pulling the needle sheath away from the green hub to expose the needle.

Do not expel any visible air bubble.

STEP 11

Pinch at least 1 inch of the area of cleaned skin with your free hand.

STEP 12

Insert the needle into subcutaneous tissue (actual angle of injection will depend on the amount of subcutaneous tissue). Do not apply pressure to the plunger.

STEP 13

Release the pinched skin once the needle is in the subcutaneous tissue.

STEP 14

Inject the Medication

- Push on the plunger using a slow, firm, and steady push until the entire dose is delivered.
- Inject the entire dose at one time, without interruption.
- Check that the plunger stopper is at the White Collar.

IMPORTANT: UZEDY is viscous. Resistance will be experienced during dose delivery. Do not use excessive force in an attempt to deliver UZEDY faster.

STEP 15

Wait 2-3 seconds after the entire dose is delivered before removing the needle. Slowly pull the needle out from the injection site at the same angle as insertion.

STEP 16

Activate (lock) the safety needle shield using one of the following methods:

- Surface Activation: Place the needle shield on a flat surface and pull the syringe backward until the needle shield covers the needle tip.

- Finger/Thumb Activation: Press either your thumb or finger on the needle shield and push it forward until the needle shield covers the needle tip.

There will be an audible click when the needle safety shield is locked.

Dispose of all syringe components in a suitable sharps container.

3 DOSAGE FORMS AND STRENGTHS

Extended-release injectable suspension: sterile, white to off-white opaque viscous suspension available in the following strengths of risperidone: 50 mg/0.14 mL, 75 mg/0.21 mL, 100 mg/0.28 mL, 125 mg/0.35 mL, 150 mg/0.42 mL, 200 mg/0.56 mL, and 250 mg/0.7 mL.

4 CONTRAINDICATIONS

UZEDY is contraindicated in patients with a known hypersensitivity to risperidone, its metabolite, paliperidone, or to any of its components. Hypersensitivity reactions, including anaphylactic reactions and angioedema, have been reported in patients treated with risperidone or paliperidone.

5 WARNINGS AND PRECAUTIONS

5.1 Increased Mortality in Elderly Patients with Dementia-Related Psychosis

Elderly patients with dementia-related psychosis treated with antipsychotic drugs are at an increased risk of death. Analyses of 17 placebo-controlled trials (modal duration of 10 weeks), largely in patients taking atypical antipsychotic drugs, revealed a risk of death in drug-treated patients of between 1.6- to 1.7-times the risk of death in placebo-treated patients. Over the course of a typical 10-week controlled trial, the rate of death in drug-treated patients was about 4.5%, compared to a rate of about 2.6% in the placebo group. Although the causes of death were varied, most of the deaths appeared to be either cardiovascular (e.g., heart failure, sudden death) or infectious (e.g., pneumonia) in nature. Observational studies suggest that, similar to atypical antipsychotic drugs, treatment with conventional antipsychotic drugs may increase mortality. The extent to which the findings of increased mortality in observational studies may be attributed to the antipsychotic drug as opposed to some characteristic(s) of the patients is not clear.

In two of four placebo-controlled trials in elderly patients with dementia-related psychosis, a higher incidence of mortality was observed in patients treated with furosemide plus oral risperidone when compared to patients treated with oral risperidone alone or with placebo plus furosemide. No pathological mechanism has been identified to explain this finding, and no consistent pattern for cause of death was observed.

UZEDY is not approved for the treatment of patients with dementia-related psychosis [see Boxed Warning and Warnings and Precautions (5.2)].

5.2 Cerebrovascular Adverse Reactions, Including Stroke, in Elderly Patients with Dementia-Related Psychosis

Cerebrovascular adverse reactions (e.g., stroke, transient ischemic attack), including fatalities, were reported in patients (mean age 85 years; range 73 to 97 years) in trials of oral risperidone in elderly patients with dementia-related psychosis. In placebo-controlled trials, there was a significantly higher incidence of cerebrovascular adverse reactions in patients treated with oral risperidone compared to patients treated with placebo. UZEDY is not approved for the treatment of patients with dementia-related psychosis [see Warnings and Precautions (5.1)].

5.3 Neuroleptic Malignant Syndrome

Neuroleptic Malignant Syndrome (NMS), a potentially fatal symptom complex, has been reported in association with antipsychotic drugs. Clinical manifestations of NMS are hyperpyrexia, muscle rigidity, altered mental status including delirium, and autonomic instability (irregular pulse or blood pressure, tachycardia, diaphoresis, and cardiac dysrhythmia). Additional signs may include elevated creatine phosphokinase, myoglobinuria (rhabdomyolysis), and acute renal failure.

If NMS is suspected, immediately discontinue UZEDY and provide symptomatic treatment and monitoring.

5.4 Tardive Dyskinesia

Tardive dyskinesia, a syndrome consisting of potentially irreversible, involuntary, dyskinetic movements may develop in patients treated with antipsychotic drugs. Although the prevalence of the syndrome appears to be highest among the elderly, especially elderly women, it is impossible to predict, which patients will develop the syndrome. Whether antipsychotic drug products differ in their potential to cause tardive dyskinesia is unknown.

The risk of developing tardive dyskinesia and the likelihood that it will become irreversible are believed to increase with the duration of treatment and the cumulative dose. The syndrome can develop, after relatively brief treatment periods, even at low doses. It may also occur after discontinuation of treatment.

Tardive dyskinesia may remit, partially or completely, if antipsychotic treatment is discontinued. Antipsychotic treatment, itself, however, may suppress (or partially suppress) the signs and symptoms of the syndrome possibly masking the underlying process. The effect that symptomatic suppression has upon the long-term course of the syndrome is unknown.

Given these considerations, UZEDY should be prescribed in a manner that is most likely to minimize the occurrence of tardive dyskinesia. Chronic antipsychotic treatment should generally be reserved for patients: (1) who suffer from a chronic illness that is known to respond to antipsychotic drugs, and (2) for whom alternative, equally effective, but potentially less harmful treatments are not available or appropriate. In patients who do require chronic treatment, use the lowest dose and the shortest duration of treatment producing a satisfactory clinical response. Periodically reassess the need for continued treatment.

If signs and symptoms of tardive dyskinesia appear in a patient treated with UZEDY, drug discontinuation should be considered. However, some patients may require treatment with UZEDY despite the presence of the syndrome.

5.5 Metabolic Changes

Atypical antipsychotic drugs have been associated with metabolic changes that may increase cardiovascular/cerebrovascular risk. These metabolic changes include hyperglycemia, dyslipidemia, and body weight gain. While all of the drugs in the class have been shown to produce some metabolic changes, each drug has its own specific risk profile.

Hyperglycemia and Diabetes Mellitus

Hyperglycemia and diabetes mellitus, in some cases extreme and associated with ketoacidosis or hyperosmolar coma or death, have been reported in patients treated with atypical antipsychotics including risperidone. Assessment of the relationship between atypical antipsychotic use and glucose abnormalities is complicated by the possibility of an increased background risk of diabetes mellitus in patients with schizophrenia and the increasing incidence of diabetes mellitus in the general population. Given these confounders, the relationship between atypical antipsychotic use and hyperglycemia-related adverse events is not completely understood. However, epidemiological studies suggest an increased risk of treatment-emergent hyperglycemia-related adverse events in patients treated with the atypical antipsychotics. Precise risk estimates for hyperglycemia-related adverse events in patients treated with atypical antipsychotics are not available.

Patients with an established diagnosis of diabetes mellitus who are started on atypical antipsychotics, including UZEDY, should be monitored regularly for worsening of glucose control. Patients with risk factors for diabetes mellitus (e.g., obesity, family history of diabetes) who are starting treatment with atypical antipsychotics, including UZEDY, should undergo fasting blood glucose testing at the beginning of treatment and periodically during treatment. Any patient treated with atypical antipsychotics, including UZEDY, should be monitored for symptoms of hyperglycemia including polydipsia, polyuria, polyphagia, and weakness. Patients who develop symptoms of hyperglycemia during treatment with atypical antipsychotics, including UZEDY, should undergo fasting blood glucose testing. In some cases, hyperglycemia has resolved when the atypical antipsychotic, including risperidone, was discontinued; however, some patients required continuation of antidiabetic treatment despite discontinuation of risperidone.

Pooled data from three double-blind, placebo-controlled schizophrenia studies and four double-blind, placebo-controlled studies in another indication with oral risperidone are presented in Table 4.

Table 4: Change in Random Glucose from Seven Placebo-Controlled, 3- to 8-Week, Fixed- or Flexible-Dose Studies in Adults with Schizophrenia or Another Indication with Oral Risperidone
 |  | Oral Risperidone
 | Placebo | 1 mg to 8 mg per day | >8 mg to 16 mg per day
 | Mean change from baseline (mg/dL)
Serum Glucose | N=555; -1.4 | N=748; 0.8 | N=164; 0.6
 | Proportion of Patients with Shifts
Serum Glucose; (<140 mg/dL to ≥200 mg/dL) | 0.6%; (3/525) | 0.4%; (3/702) | 0%; (0/158)

In longer-term, controlled and uncontrolled studies in adults, oral risperidone was associated with a mean change in glucose of +2.8 mg/dL at Week 24 (N=151) and +4.1 mg/dL at Week 48 (N=50).

Dyslipidemia

Undesirable alterations in lipids have been observed in patients treated with atypical antipsychotics. Before or soon after initiation of antipsychotic medications, obtain a fasting lipid profile at baseline and monitor periodically during treatment.

Pooled data from 7 placebo-controlled, 3- to 8- week, fixed- or flexible-dose studies in adults with schizophrenia or another indication with oral risperidone are presented in Table 5.

Table 5: Change in Random Lipids from Seven Placebo-Controlled, 3- to 8-Week, Fixed- or Flexible-Dose Studies in Adults with Schizophrenia or Another Indication with Oral Risperidone
 |  | Oral Risperidone
 | Placebo | 1 mg to 8 mg per day | >8 mg to 16 mg per day
 | Mean change from baseline (mg/dL)
Cholesterol; Change from baseline | N=559; 0.6 | N=742; 6.9 | N=156; 1.8
Triglycerides; Change from baseline | N=183; -17.4 | N=307; -4.9 | N=123; -8.3
 | Proportion of Patients with Shifts
Cholesterol; (<200 mg/dL to ≥240 mg/dL) | 2.7%; (10/368) | 4.3%; (22/156) | 6.3%; (6/96)
Triglycerides; (<500 mg/dL to ≥500 mg/dL) | 1.1%; (2/180) | 2.7%; (8/301) | 2.5%; (3/121)

In longer-term, controlled and uncontrolled studies, oral risperidone was associated with a mean change in (a) non-fasting cholesterol of +4.4 mg/dL at Week 24 (N=231) and +5.5 mg/dL at Week 48 (N=86); and (b) non-fasting triglycerides of +19.9 mg/dL at Week 24 (N=52).

Weight Gain

Weight gain has been observed with atypical antipsychotic use. Clinical monitoring of weight is recommended.

Data on mean changes in body weight and the proportion of subjects meeting a weight gain criterion of 7% or greater of body weight from 7 placebo-controlled, 3- to 8- week, fixed- or flexible-dose studies in adults with schizophrenia or another indication with oral risperidone are presented in Table 6.

Table 6: Mean Change in Body Weight (kg) and the Proportion of Subjects with ≥7% Gain in Body Weight From Seven Placebo-Controlled, 3- to 8-Week, Fixed- or Flexible-Dose Studies in Adults With Schizophrenia or Another Indication with Oral Risperidone
 |  | Oral Risperidone
 | Placebo; (n=597) | 1 mg to 8 mg per day; (n=769) | >8 mg to 16 mg per day; (n=158)
Weight (kg); Change from baseline | -0.3 | 0.7 | 2.2
Weight Gain; ≥7% increase from baseline | 2.9% | 8.7% | 20.9%

In longer-term, controlled and uncontrolled studies, oral risperidone was associated with a mean change in weight of +4.3 kg at Week 24 (n=395) and +5.3 kg at Week 48 (n=203).

5.6 Hyperprolactinemia

As with other drugs that antagonize dopamine D2 receptors, risperidone elevates prolactin levels and the elevation persists during chronic administration. Risperidone is associated with higher levels of prolactin elevation than other antipsychotic agents.

Hyperprolactinemia may suppress hypothalamic GnRH, resulting in reduced pituitary gonadotropin secretion. This in turn may inhibit reproductive function by impairing gonadal steroidogenesis in both female and male patients. Galactorrhea, amenorrhea, gynecomastia, and impotence have been reported in patients receiving prolactin-elevating compounds. Long-standing hyperprolactinemia may lead to decreased bone density in both female and male patients.

Tissue culture experiments indicate that approximately one-third of human breast cancers are prolactin dependent in vitro, a factor of potential importance if the prescription of these drugs is contemplated in a patient with previously detected breast cancer. An increase in pituitary gland, mammary gland, and pancreatic islet cell neoplasia (mammary adenocarcinomas, pituitary and pancreatic adenomas) was observed in the risperidone carcinogenicity studies conducted in mice and rats [see Nonclinical Toxicology (13.1)]. Published epidemiologic studies have shown inconsistent results when exploring the potential association between hyperprolactinemia and breast cancer.

5.7 Orthostatic Hypotension and Syncope

UZEDY may induce orthostatic hypotension associated with dizziness, tachycardia, and in some patients, syncope, probably reflecting its alpha-adrenergic antagonistic properties. Syncope was reported in 0.2% (6/2607) of patients treated with oral risperidone in Phase 2 and 3 studies in adults with schizophrenia.

UZEDY should be used with particular caution in (1) patients with known cardiovascular disease (history of myocardial infarction or ischemia, heart failure, or conduction abnormalities), cerebrovascular disease, and conditions which would predispose patients to hypotension, e.g., dehydration and hypovolemia and (2) in the elderly and patients with renal or hepatic impairment. Monitoring of orthostatic vital signs should be considered in all such patients, and a dose reduction should be considered if hypotension occurs. Clinically significant hypotension has been observed with concomitant use of oral risperidone and antihypertensive medication.

5.8 Falls

Antipsychotics, including UZEDY, may cause somnolence, postural hypotension, motor and sensory instability which may lead to falls and, consequently, fractures or other fall-related injuries. Somnolence, postural hypotension, motor and sensory instability have been reported with the use of risperidone. For patients, particularly the elderly, with diseases, conditions, or medications that could exacerbate these effects, assess the risk of falls when initiating antipsychotic treatment and recurrently for patients on long-term antipsychotic therapy.

5.9 Leukopenia, Neutropenia, and Agranulocytosis

In clinical trial and/or postmarketing experience, events of leukopenia/neutropenia have been reported temporally related to antipsychotic agents, including risperidone. Agranulocytosis has also been reported.

Possible risk factors for leukopenia/neutropenia include pre-existing low white blood cell count (WBC) and a history of drug-induced leukopenia/neutropenia. In patients with a pre-existing history of a clinically significant low WBC or ANC or a history of drug-induced leukopenia or neutropenia, perform a complete blood count (CBC) frequently during the first few months of therapy. In such patients, consider discontinuation of UZEDY at the first sign of a clinically significant decline in WBC in the absence of other causative factors.

Monitor patients with clinically significant neutropenia for fever or other symptoms or signs of infection and treated promptly if such symptoms or signs occur. Discontinue UZEDY in patients with absolute neutrophil count <1000/mm^3 and follow their WBC followed until recovery.

5.10 Potential for Cognitive and Motor Impairment

UZEDY, like other antipsychotics, may cause somnolence and has the potential to impair judgement, thinking, and motor skills. Somnolence was a commonly reported adverse reaction associated with oral risperidone treatment, especially when ascertained by direct questioning of patients. This adverse reaction is dose-related, and in a study utilizing a checklist to detect adverse reactions, 41% of the high-dose patients (oral risperidone 16 mg/day) reported somnolence compared to 16% of placebo patients. Direct questioning is more sensitive for detecting adverse reactions than spontaneous reporting, by which 8% of oral risperidone 16 mg/day patients and 1% of placebo patients reported somnolence as an adverse reaction.

Patients should be cautioned about operating hazardous machinery, including motor vehicles, until they are reasonably certain that treatment with UZEDY does not affect them adversely.

5.11 Seizures

During premarketing studies, seizures occurred in 0.3% of patients (9 out of 2,607 in adult patients with schizophrenia treated with oral risperidone [two in association with hyponatremia] and 5 out of 1,499 treated with another risperidone long-acting injection given once every 2 weeks). Use UZEDY cautiously in patients with a history of seizures or other conditions that potentially lower the seizure threshold.

5.12 Dysphagia

Esophageal dysmotility and aspiration have been associated with antipsychotic drug use. Aspiration pneumonia is a common cause of morbidity and mortality in patients with advanced Alzheimer’s dementia. Antipsychotic drugs, including UZEDY, should be used cautiously in patients at risk for aspiration.

5.13 Priapism

Priapism has been reported during postmarketing surveillance for other risperidone products. A case of priapism was reported in premarket studies of UZEDY. Severe priapism may require surgical intervention.

5.14 Body Temperature Regulation

Disruption of the body’s ability to reduce core body temperature has been attributed to antipsychotic agents. Both hyperthermia and hypothermia have been reported in association with oral risperidone use. Strenuous exercise, exposure to extreme heat, dehydration, and anticholinergic medications may contribute to an elevation in core body temperature; use UZEDY with caution in patients who may experience these conditions.

6 ADVERSE REACTIONS

The following are discussed in more detail in other sections of the labeling:

- Increased mortality in elderly patients with dementia-related psychosis [see Boxed Warning and Warnings and Precautions (5.1)]
- Cerebrovascular adverse events, including stroke, in elderly patients with dementia-related psychosis [see Warnings and Precautions (5.2)]
- Neuroleptic malignant syndrome [see Warnings and Precautions (5.3)]
- Tardive dyskinesia [see Warnings and Precautions (5.4)]
- Metabolic changes [see Warnings and Precautions (5.5)]
- Hyperprolactinemia [see Warnings and Precautions (5.6)]
- Orthostatic hypotension and syncope [see Warnings and Precautions (5.7)]
- Falls [see Warnings and Precautions (5.8)]
- Leukopenia, neutropenia and agranulocytosis [see Warnings and Precautions (5.9)]
- Potential for cognitive and motor impairment [see Warnings and Precautions (5.10)]
- Seizures [see Warnings and Precautions (5.11)]
- Dysphagia [see Warnings and Precautions (5.12)]
- Priapism [see Warnings and Precautions (5.13)]
- Body temperature regulation [see Warnings and Precautions (5.14)]

6.1 Clinical Trials Experience

Because clinical trials are conducted under widely varying conditions, adverse reaction rates observed in the clinical trials of a drug cannot be directly compared to rates in the clinical trials of another drug and may not reflect the rates observed in clinical practice.

Treatment of Schizophrenia in Adults

UZEDY is to be administered subcutaneously [see Dosage and Administration (2.1)]. The safety of UZEDY for the treatment of schizophrenia in adults is based on adequate and well-controlled studies of oral risperidone in studies of patients with schizophrenia and other indications. The results of those adequate and well-controlled studies are presented below.

The data described in this section are derived from a clinical trial database consisting of 9,803 patients exposed to one or more doses of oral risperidone for the treatment of schizophrenia and other psychiatric disorders. Of these 9,803 patients, 2,687 were patients who received oral risperidone while participating in double-blind, placebo-controlled trials. The conditions and duration of treatment with oral risperidone varied greatly and included (in overlapping categories) double-blind, fixed- and flexible-dose, placebo- or active-controlled studies and open-label phases of studies, inpatients and outpatients, and short-term (up to 12 weeks) and longer-term (up to 3 years) exposures. Safety was assessed by collecting adverse reactions and performing physical examinations, vital signs, body weights, laboratory analyses, and ECGs.

Injection site reactions for UZEDY presented in this section (see “Injection Site Reactions with UZEDY” below) are based on a randomized withdrawal study in patients with schizophrenia consisting of a 12-week open-label oral risperidone (2 mg to 5 mg) stabilization phase, followed by a placebo-controlled phase in which patients were randomized to UZEDY (once monthly or once every 2 months) or placebo for a variable time until impending relapse or study completion [see Clinical Studies (14)].

The safety of UZEDY was evaluated in a total of 740 adult patients with schizophrenia who received at least 1 dose of UZEDY during the clinical development program. A total of 351 patients were exposed to UZEDY for at least 6 months, of which 221 patients were exposed to UZEDY for at least 12 months, which included 112 patients exposed to once monthly and 109 patients to once every 2 months dosing regimens. In addition, 32 patients were exposed to UZEDY for at least 24 months.

Treatment of Bipolar Disorder in Adults

UZEDY is to be administered subcutaneously [see Dosage and Administration (2.1)]. The data presented below are from studies with another risperidone long-acting injection given once every 2 weeks that was administered intramuscularly.

The safety of UZEDY as monotherapy or as adjunctive therapy to lithium or valproate for the maintenance treatment of Bipolar I Disorder in adults is based on adequate and well-controlled studies of another risperidone long-acting injection given once every 2 weeks. The results of those adequate and well-controlled studies are presented below.

Safety data are presented from a trial assessing the efficacy and safety of another risperidone long-acting injection, given once every 2 weeks, when administered as monotherapy for maintenance treatment in patients with bipolar I disorder.

Safety data are also presented from a trial assessing the efficacy and safety of another risperidone long-acting injection, given once every 2 weeks, administered as adjunctive maintenance treatment in patients with bipolar disorder.

Adverse Reactions in Studies with Oral Risperidone

The most common adverse reactions in clinical trials of oral risperidone (>5% and twice placebo) were parkinsonism, akathisia, dystonia, tremor, sedation, dizziness, anxiety, blurred vision, nausea, vomiting, upper abdominal pain, stomach discomfort, dyspepsia, diarrhea, salivary hypersecretion, constipation, dry mouth, increased appetite, increased weight, fatigue, rash, nasal congestion, upper respiratory tract infection, nasopharyngitis, and pharyngolaryngeal pain.

Commonly-Observed Adverse Reactions in Double-Blind, Placebo-Controlled Clinical Trials – Adult Patients with Schizophrenia Treated with Oral Risperidone

Table 7 lists the adverse reactions reported in 2% or more of oral risperidone-treated adult patients with schizophrenia in three 4- to 8-week, double-blind, placebo-controlled trials.

Table 7: Adverse Reactions in ≥2% of Oral Risperidone-Treated Adult Patients (and greater than placebo) with Schizophrenia in Double-Blind, Placebo-Controlled Trials
 | Percentage of Patients Reporting Reaction
 | Oral Risperidone
System/Organ Class; Adverse Reaction | 2 mg to 8 mg per day (N=366) | >8 mg to 16 mg per day (N=198) | Placebo (N=225)
Cardiac Disorders
Tachycardia | 1 | 3 | 0
Eye Disorders
Vision blurred | 3 | 1 | 1
Gastrointestinal Disorders
Nausea | 9 | 4 | 4
Constipation | 8 | 9 | 6
Dyspepsia | 8 | 6 | 5
Dry mouth | 4 | 0 | 1
Abdominal discomfort | 3 | 1 | 1
Salivary hypersecretion | 2 | 1 | <1
Diarrhea | 2 | 1 | 1
General Disorders
Fatigue | 3 | 1 | 0
Chest pain | 2 | 2 | 1
Asthenia | 2 | 1 | <1
Infections and Infestations
Nasopharyngitis | 3 | 4 | 3
Upper respiratory tract infection | 2 | 3 | 1
Sinusitis | 1 | 2 | 1
Urinary tract infection | 1 | 3 | 0
Investigations
Blood creatine phosphokinase increased | 1 | 2 | <1
Heart rate increased | <1 | 2 | 0
Musculoskeletal and Connective Tissue Disorders
Back pain | 4 | 1 | 1
Arthralgia | 2 | 3 | <1
Pain in extremity | 2 | 1 | 1
Nervous System Disorders
Parkinsonism* | 14 | 17 | 8
Akathisia* | 10 | 10 | 3
Sedation | 10 | 5 | 2
Dizziness | 7 | 4 | 2
Dystonia* | 3 | 4 | 2
Tremor* | 2 | 3 | 1
Dizziness postural | 2 | 0 | 0
Psychiatric Disorders
Insomnia | 32 | 25 | 27
Anxiety | 16 | 11 | 11
Respiratory, Thoracic and Mediastinal Disorders
Nasal congestion | 4 | 6 | 2
Dyspnea | 1 | 2 | 0
Epistaxis | <1 | 2 | 0
Skin and Subcutaneous Tissue Disorders
Rash | 1 | 4 | 1
Dry skin | 1 | 3 | 0
Vascular Disorders
Orthostatic hypotension | 2 | 1 | 0

* Parkinsonism includes extrapyramidal disorder, musculoskeletal stiffness, parkinsonism, cogwheel rigidity, akinesia, bradykinesia, hypokinesia, masked facies, muscle rigidity, and Parkinson’s disease. Akathisia includes akathisia and restlessness. Dystonia includes dystonia, muscle spasms, muscle contractions involuntary, muscle contracture, oculogyration, tongue paralysis. Tremor includes tremor and parkinsonian rest tremor.

Adverse Reactions in Studies with Another Long-Acting Injection Risperidone, Given Once Every 2 Weeks

The most common adverse reactions in the double-blind, placebo-controlled periods of the bipolar disorder trials of another risperidone long-acting injection were weight increased (5% in the monotherapy trial) and tremor and parkinsonism (≥ 10% in the adjunctive treatment trial).

Commonly-Observed Adverse Reactions in Double-Blind, Placebo-Controlled Clinical Trials – Adult Patients with Bipolar Disorder Treated with Another Risperidone Long-Acting Injection Given Once Every 2 Weeks

Table 8 lists the treatment-emergent adverse reactions reported in 2% or more of patients treated with another risperidone long-acting injection, given once every 2 weeks, in the 24-month double-blind, placebo-controlled treatment period of the trial assessing the efficacy and safety of another risperidone long-acting injection when administered as monotherapy for maintenance treatment in patients with bipolar I disorder.

Table 8: Adverse Reactions in ≥2% of Adult Patients with Bipolar I Disorder Treated with Another Risperidone Long-Acting Injection, Given Once Every 2 Weeks, as Monotherapy in a 24-Month Double-Blind, Placebo-Controlled Trial
 | Percentage of Patients Reporting Event
System/Organ Class Adverse Reaction | Risperidone Long-Acting Injectiona (N=154) | Placebo; (N=149)
Investigations
Weight increased | 5 | 1
Nervous system disorders
Dizziness | 3 | 1
Vascular disorders
Hypertension | 3 | 1

a The data presented are from a study with another risperidone long-acting injection that was administered once every 2 weeks, intramuscularly. UZEDY is to be administered subcutaneously.

Table 9 lists the treatment-emergent adverse reactions reported in 4% or more of patients in the 52-week double-blind, placebo-controlled treatment phase of a trial assessing the efficacy and safety of another Risperidone Long-Acting Injection, given once every 2 weeks, when administered as adjunctive maintenance treatment in patients with bipolar disorder.

Table 9: Adverse Reactions Occurring in ≥4% of Adult Patients with Bipolar I Disorder Treated with Another Risperidone Long-Acting Injection, Given Once Every 2 Weeks, as Adjunctive Therapy in a 52-Week Double-Blind, Placebo-Controlled Trial
 | Percentage of Patients Reporting Event
System/Organ Class Adverse Reaction | Risperidone Long-Acting Injectiona + Treatment as Usualb (N=72) | Placebo + Treatment as Usualb; (N=67)
General disorders and administration site conditions
Gait abnormal | 4 | 0
Infections and infestations
Upper respiratory tract infection | 6 | 3
Investigations
Weight increased | 7 | 1
Metabolism and nutrition disorders
Decreased appetite | 6 | 1
Increased appetite | 4 | 0
Musculoskeletal and connective tissue disorders
Arthralgia | 4 | 3
Nervous system disorders
Tremor | 24 | 16
Parkinsonismc | 15 | 6
Dyskinesiad | 6 | 3
Sedatione | 7 | 1
Disturbance in attention | 4 | 0
Reproductive system and breast disorders
Amenorrhea | 4 | 1
Respiratory, thoracic and mediastinal disorders
Cough | 4 | 1

a The data presented are from a study with another risperidone long-acting injection that was administered once every 2 weeks, intramuscularly. UZEDY is to be administered subcutaneously.
b Patients received double-blind treatment with another risperidone long-acting injection, given once every 2 weeks, or placebo in addition to continuing their treatment as usual, which included mood stabilizers, antidepressants, and/or anxiolytics.
c Parkinsonism includes muscle rigidity, hypokinesia, cogwheel rigidity, and bradykinesia.
d Dyskinesia includes muscle twitching and dyskinesia.
e Sedation includes sedation and somnolence.

Other Adverse Reactions Observed During the Clinical Trial Evaluations of Oral Risperidone

The following is a list of additional adverse drug reactions that have been reported during the clinical trial evaluation of oral risperidone:

Blood and Lymphatic System Disorders: anemia, granulocytopenia, neutropenia

Cardiac Disorders: sinus bradycardia, sinus tachycardia, atrioventricular block first degree, bundle branch block left, bundle branch block right, atrioventricular block

Ear and Labyrinth Disorders: ear pain, tinnitus

Endocrine Disorders: hyperprolactinemia

Eye Disorders: ocular hyperemia, eye discharge, conjunctivitis, eye rolling, eyelid edema, eye swelling, eyelid margin crusting, dry eye, lacrimation increased, photophobia, glaucoma, visual acuity reduced

Gastrointestinal Disorders: dysphagia, fecaloma, fecal incontinence, gastritis, lip swelling, cheilitis, aptyalism

General Disorders: edema peripheral, thirst, gait disturbance, chest discomfort, chest pain, influenza-like illness, pitting edema, edema, chills, sluggishness, malaise, face edema, discomfort, generalized edema, drug withdrawal syndrome, peripheral coldness, feeling abnormal

Immune System Disorders: drug hypersensitivity

Infections and Infestations: pneumonia, influenza, ear infection, viral infection, pharyngitis, tonsillitis, bronchitis, eye infection, localized infection, cystitis, cellulitis, otitis media, onychomycosis, acarodermatitis, bronchopneumonia, respiratory tract infection, tracheobronchitis, otitis media chronic

Investigations: body temperature increased, blood prolactin increased, alanine aminotransferase increased, electrocardiogram abnormal, eosinophil count increased, white blood cell count decreased, blood glucose increased, hemoglobin decreased, hematocrit decreased, body temperature decreased, blood pressure decreased, transaminases increased

Metabolism and Nutrition Disorders: decreased appetite, polydipsia, anorexia

Musculoskeletal, Connective Tissue, and Bone Disorders: joint swelling, joint stiffness, musculoskeletal chest pain, posture abnormal, myalgia, neck pain, muscular weakness, muscle rigidity, rhabdomyolysis, torticollis

Nervous System Disorders: balance disorder, disturbance in attention, dysarthria, unresponsive to stimuli, depressed level of consciousness, movement disorder, transient ischemic attack, coordination abnormal, cerebrovascular accident, speech disorder, syncope, loss of consciousness, hypoesthesia, tardive dyskinesia, cerebral ischemia, cerebrovascular disorder, neuroleptic malignant syndrome, diabetic coma, head titubation

Psychiatric Disorders: agitation, blunted affect, confusional state, middle insomnia, nervousness, sleep disorder, listlessness, libido decreased, anorgasmia

Renal and Urinary Disorders: enuresis, dysuria, pollakiuria, urinary incontinence

Reproductive System and Breast Disorders: menstruation irregular, amenorrhea, gynecomastia, galactorrhea, vaginal discharge, menstrual disorder, erectile dysfunction, retrograde ejaculation, ejaculation disorder, sexual dysfunction, breast enlargement

Respiratory, Thoracic, and Mediastinal Disorders: wheezing, pneumonia aspiration, sinus congestion, dysphonia, productive cough, pulmonary congestion, respiratory tract congestion, rales, respiratory disorder, hyperventilation, nasal edema

Skin and Subcutaneous Tissue Disorders: erythema, skin discoloration, skin lesion, pruritus, skin disorder, rash erythematous, rash papular, acne, hyperkeratosis, seborrheic dermatitis, rash generalized, rash maculopapular

Vascular Disorders: hypotension, flushing

Additional Adverse Reactions Reported With Another Risperidone Long-Acting Injection, Given Once Every 2 Weeks

The following is a list of additional adverse reactions that have been reported during the premarketing evaluation of another risperidone long-acting injection, given once every 2 weeks, regardless of frequency of occurrence:

Cardiac Disorders: bradycardia, tachycardia, palpitations

Ear and Labyrinth Disorders: vertigo

Eye Disorders: blepharospasm

Gastrointestinal Disorders: toothache, tongue spasm, diarrhea, vomiting, abdominal pain upper, abdominal pain, stomach discomfort

General Disorders and Administration Site Conditions: pain, injection site pain, induration, injection site induration, injection site swelling, injection site reaction

Infections and Infestations: lower respiratory tract infection, infection, gastroenteritis, subcutaneous abscess, nasopharyngitis, urinary tract infection, rhinitis, sinusitis

Injury and Poisoning: fall, procedural pain

Investigations: weight decreased, gamma-glutamyltransferase increased, hepatic enzyme increased, aspartate aminotransferase increased, electrocardiogram QT prolonged, glucose urine present

Musculoskeletal, Connective Tissue, and Bone Disorders: buttock pain, back pain

Nervous System Disorders: convulsion, paresthesia, dystonia, drooling, dizziness postural, akinesia, hypokinesia

Psychiatric Disorders: depression, insomnia, anxiety, initial insomnia

Reproductive System and Breast Disorders: oligomenorrhea, breast discomfort, menstruation delayed, ejaculation delayed

Respiratory, Thoracic, and Mediastinal Disorders: nasal congestion, pharyngolaryngeal pain, dyspnea, rhinorrhea

Skin and Subcutaneous Tissue Disorders: eczema, rash, pruritis generalized

Vascular Disorders: hypertension, orthostatic hypotension

Discontinuations Due to Adverse Drug Reactions with Oral Risperidone

Schizophrenia

Approximately 7% (39/564) of oral risperidone-treated patients in double-blind, placebo-controlled trials discontinued treatment due to an adverse reaction, compared with 4% (10/225) who were receiving placebo. The adverse reactions associated with discontinuation in 2 or more oral risperidone-treated patients were:

Table 10: Adverse Reactions Associated with Discontinuation in ≥2% of Oral Risperidone-Treated Adult Patients in Schizophrenia Trials
 | Oral Risperidone
Adverse Reaction | 2 mg to 8 mg per day; (N=366) | >8 mg to 16 mg per day; (N=198) | Placebo; (N=225)
Dizziness | 1.4% | 1% | 0%
Nausea | 1.4% | 0% | 0%
Vomiting | 0.8% | 0% | 0%
Parkinsonism | 0.8% | 0% | 0%
Somnolence | 0.8% | 0% | 0%
Dystonia | 0.5% | 0% | 0%
Agitation | 0.5% | 0% | 0%
Abdominal pain | 0.5% | 0% | 0%
Orthostatic hypotension | 0.3% | 0.5% | 0%
Akathisia | 0.3% | 2% | 0%

Discontinuation for extrapyramidal symptoms (including Parkinsonism, akathisia, dystonia, and tardive dyskinesia) was 1% in placebo-treated patients, and 3.4% in active control-treated patients in a double-blind, placebo- and active-controlled trial.

Discontinuations Due to Adverse Drug Reactions with Another Long-Acting Injection Risperidone, Given Once Every 2 Weeks

Bipolar Disorder

In a 24-month double-blind, placebo-controlled treatment period of the trial assessing the efficacy and safety of another risperidone long-acting injection, given once every 2 weeks, monotherapy for maintenance treatment in patients with bipolar I disorder, 1 (0.6%) of 154 patients treated with another risperidone long-acting injection, given once every 2 weeks, discontinued due to an adverse reaction (hyperglycemia).

In the 52-week double-blind phase of the placebo-controlled trial in which patients treated with another risperidone long-acting injection, given once every 2 weeks, was administered as adjunctive therapy to patients with bipolar disorder in addition to continuing with their usual treatment, approximately 4% (3/72) of patients treated with another risperidone long-acting injection, given once every 2 weeks, discontinued treatment due to an adverse event, compared with 1.5% (1/67) of placebo-treated patients. Adverse reactions associated with discontinuation in patients treated with another risperidone long-acting injection, given once every 2 weeks, were hypokinesia (one patient) and tardive dyskinesia (one patient).

Dose Dependency of Adverse Reactions in Clinical Trials of Oral Risperidone

Extrapyramidal Symptoms

Data from two fixed-dose trials in adults with schizophrenia provided evidence of dose-relatedness for extrapyramidal symptoms associated with oral risperidone treatment. Two methods were used to measure extrapyramidal symptoms (EPS) in an 8-week trial comparing 4 fixed doses of oral risperidone (2, 6, 10, and 16 mg/day), including (1) a Parkinsonism score (mean change from baseline) from the Extrapyramidal Symptom Rating Scale, and (2) incidence of spontaneous complaints of EPS:

Table 11: Extrapyramidal Symptoms Associated with Oral Risperidone-Treated Adult Patients in an 8-Week Fixed Dose Schizophrenia Trial
Dose Groups | Placebo | Oral Risperidone; 2 mg | Oral Risperidone; 6 mg | Oral Risperidone; 10 mg | Oral Risperidone; 16 mg
Parkinsonism | 1.2 | 0.9 | 1.8 | 2.4 | 2.6
EPS Incidence | 13% | 17% | 21% | 21% | 35%

Similar methods were used to measure extrapyramidal symptoms (EPS) in an 8-week trial comparing 5 fixed doses of oral risperidone (1, 4, 8, 12, and 16 mg/day):

Table 12: Extrapyramidal Symptoms Associated with Oral Risperidone-Treated Adult Patients in an 8-Week Fixed Dose Schizophrenia Trial
Dose Groups | Oral Risperidone; 1 mg | Oral Risperidone; 4 mg | Oral Risperidone; 8 mg | Oral Risperidone; 12 mg | Oral Risperidone; 16 mg
Parkinsonism | 0.6 | 1.7 | 2.4 | 2.9 | 4.1
EPS Incidence | 7% | 12% | 17% | 18% | 20%

Changes in Body Weight

Weight gain was observed in short-term, controlled trials and longer-term uncontrolled studies in adults [see Warnings and Precautions (5.5) and Adverse Reactions (6)].

Dystonia

Symptoms of dystonia, prolonged abnormal contractions of muscle groups, may occur in susceptible individuals during the first few days of treatment. Dystonic symptoms include: spasm of the neck muscles, sometimes progressing to tightness of the throat, swallowing difficulty, difficulty breathing, and/or protrusion of the tongue. While these symptoms can occur at low doses, they occur more frequently and with greater severity with high potency and at higher doses of first generation antipsychotic drugs. An elevated risk of acute dystonia is observed in males and younger age groups.

Other Adverse Reactions

Adverse reaction data elicited by a checklist for side effects from a large study comparing 5 fixed doses of oral risperidone (1, 4, 8, 12, and 16 mg/day) were explored for dose-relatedness of adverse events. A Cochran-Armitage Test for trend in these data revealed a positive trend (p<0.05) for the following adverse reactions: somnolence, vision abnormal, dizziness, palpitations, weight increase, erectile dysfunction, ejaculation disorder, sexual function abnormal, fatigue, and skin discoloration.

Changes in ECG

Between-group comparisons for pooled placebo-controlled trials of oral risperidone in adults revealed no statistically significant differences between oral risperidone and placebo in mean changes from baseline in ECG parameters, including QT, QTc, and PR intervals, and heart rate. When all oral risperidone doses were pooled from randomized controlled trials in several indications, there was a mean increase in heart rate of 1 beat per minute compared to no change for placebo patients. In short-term schizophrenia trials, higher doses of oral risperidone were associated with a higher mean increase in heart rate compared to placebo (4 to 6 beats per minute).

The ECGs of 227 patients with Bipolar I Disorder were evaluated in the 24-month double-blind, placebo-controlled period. There were no clinically relevant differences in QTc intervals (using Fridericia's and linear correction factors) during treatment with another risperidone long-acting injection, given once every 2 weeks, compared to placebo.

The ECGs of 85 patients with bipolar disorder were evaluated in the 52-week double-blind, placebo-controlled trial. There were no statistically significant differences in QTc intervals (using Fridericia's and linear correction factors) during adjunctive treatment with either another risperidone long-acting injection (25 mg, 37.5 mg, or 50 mg), given once every 2 weeks, or placebo in addition to treatment as usual.

Injection Site Reactions with UZEDY

Local tolerability assessments were administered to patients who reported injection site adverse reactions in a randomized withdrawal study with UZEDY in adult patients with schizophrenia. The injection site was assessed by appropriately trained personnel throughout the clinical development program.

All injection site reactions (nodule, pruritus, erythema, mass, and swelling) were mild to moderate in severity with the exception of 1 case of severe pruritus which resolved after 6 days. Injection site reactions were reported in 22 patients (13%) in the placebo group, 36 patients (20%) in the UZEDY once monthly group, and 37 patients (21%) in the UZEDY once every 2 months group. The most common injection site reactions were: nodule (7% in each UZEDY-treated group and 3% in the placebo group) and pruritus (5% and 3% in the UZEDY-treated once monthly and once every 2 months groups, respectively, and 2% in the placebo group).

6.2 Postmarketing Experience

The following adverse reactions have been identified during post-approval use of oral risperidone. Because these reactions are reported voluntarily from a population of uncertain size, it is not always possible to reliably estimate their frequency or establish a causal relationship to drug exposure.

These adverse reactions include: alopecia, anaphylactic reaction, angioedema, atrial fibrillation, cardiopulmonary arrest, catatonia, diabetic ketoacidosis in patients with impaired glucose metabolism, dysgeusia, hypoglycemia, hypothermia, ileus, inappropriate antidiuretic hormone secretion, intestinal obstruction, jaundice, mania, pancreatitis, pituitary adenoma, precocious puberty, pulmonary embolism, QT prolongation, sleep apnea syndrome, somnambulism, Stevens-Johnson syndrome and toxic epidermal necrolysis (SJS/TEN), sudden death, thrombocytopenia, thrombotic thrombocytopenic purpura, urinary retention, and water intoxication.

In addition, the following adverse reactions have been observed during postapproval use of UZEDY: injection site pain.

In addition, the following adverse reactions have been observed during postapproval use of another risperidone long-acting injection, given intramuscularly once every 2 weeks: cerebrovascular disorders, including cerebrovascular accidents, and diabetes mellitus aggravated.

Retinal artery occlusion after injection of another risperidone long-acting injection, given intramuscularly once every 2 weeks, has been reported during postmarketing surveillance. This has been reported in the presence of abnormal arteriovenous anastomosis.

Serious injection site reactions including abscess, cellulitis, cyst, hematoma, necrosis, nodule, and ulcer have been reported with another risperidone long-acting injection, given intramuscularly once every 2 weeks, during postmarketing surveillance. Isolated cases required surgical intervention.

Very rarely, cases of anaphylactic reaction after injection with another risperidone long-acting injection, given intramuscularly once every 2 weeks, have been reported during postmarketing experience in patients who have previously tolerated oral risperidone.

Postmarketing cases of extrapyramidal symptoms (dystonia and dyskinesia) have been reported in patients concomitantly taking methylphenidate and risperidone when there was an increase or decrease in dosage, initiation, or discontinuation of either or both medications.

7 DRUG INTERACTIONS

The interactions of UZEDY with co-administration of other drugs have not been studied. The drug interaction data provided in this section is based on studies with oral risperidone.

7.1 Drugs Having Clinically Important Interactions with UZEDY

Table 13 includes clinically significant drug interactions with UZEDY.

Table 13: Clinically Important Drug Interactions with UZEDY
Strong CYP2D6 Inhibitors
Clinical Impact: | Concomitant use of UZEDY with strong CYP2D6 inhibitors may increase the plasma exposure of risperidone and lower the plasma exposure of a major active metabolite, 9-hydroxyrisperidone [see Clinical Pharmacology (12.3)].
Intervention: | When initiation of strong CYP2D6 inhibitors is considered, patients may be placed on the lowest dose (50 mg once monthly or 100 mg once every 2 months) of UZEDY prior to the planned start of strong CYP2D6 inhibitors to adjust for the expected increase in plasma concentrations of risperidone. When strong CYP2D6 inhibitors are initiated in patients receiving UZEDY 50 mg once monthly or 100 mg once every 2 months, it is recommended to continue treatment with the same dose unless clinical judgment necessitates interruption of UZEDY treatment. The effects of discontinuation of strong CYP2D6 inhibitors on the pharmacokinetics of risperidone and 9-hydroxyrisperidone have not been studied [see Clinical Pharmacology (12.3)].
Strong CYP3A4 Inducers
Clinical Impact: | Concomitant use of UZEDY and a strong CYP3A4 inducer may cause decreases in the combined plasma concentrations of risperidone and 9-hydroxyrisperidone which could lead to decreased efficacy of UZEDY [see Clinical Pharmacology (12.3)].
Intervention: | Changes in efficacy and safety should be carefully monitored with any dose adjustment of UZEDY. At the initiation of therapy with a strong CYP3A4 inducer, patients should be closely monitored during the first 4 to 8 weeks. In patients receiving UZEDY at a specific dose, consider increasing the dose to the next highest dose. In patients receiving UZEDY 125 mg once monthly or 250 mg once every 2 months, additional oral risperidone therapy may need to be considered. On discontinuation of a strong CYP3A4 inducer, the dosage of UZEDY or any additional oral risperidone therapy should be reevaluated and, if necessary, decreased to adjust for the expected increase in plasma concentration of risperidone and 9-hydroxyrisperidone. For patients treated with UZEDY 50 mg once monthly or UZEDY 100 mg once every 2 months discontinuing from a strong CYP3A4 inducer, it is recommended to continue treatment with the same dose unless clinical judgment necessitates interruption of UZEDY treatment [see Dosage and Administration (2.6)].
Centrally-Acting Drugs and Alcohol
Clinical Impact: | Due to additive pharmacologic effects, the concomitant use of centrally-acting drugs, including alcohol, may increase nervous system disorders.
Intervention: | Caution should be used when UZEDY is administered in combination with other centrally-acting drugs or alcohol.
Hypotensive Agents
Clinical Impact: | Because of its potential for inducing hypotension, UZEDY may enhance the hypotensive effects of other therapeutic agents with this potential.
Intervention: | Caution should be used when UZEDY is administered with other therapeutic effects of other therapeutic agents with this potential.
Dopamine Agonists
Clinical Impact: | Agents with central antidopaminergic activity such as UZEDY may antagonize the pharmacologic effects of dopamine agonists.
Intervention: | Caution should be used when UZEDY is administered in combination with levodopa and dopamine agonists.
Methylphenidate
Clinical Impact: | Concomitant use with methylphenidate, when there is change in dosage of either medication, may increase the risk of extrapyramidal symptoms (EPS) [see Adverse Reactions (6.2)].
Intervention: | Monitor for symptoms of EPS with concomitant use of UZEDY and methylphenidate.

7.2 Drugs Having No Clinically Important Interactions with UZEDY

Based on pharmacokinetic studies with oral risperidone, no dosage adjustment of UZEDY is required when administered concomitantly with amitriptyline, cimetidine, ranitidine, clozapine, topiramate, and moderate CYP3A4 inhibitors (erythromycin). Additionally, no dosage adjustment is necessary for lithium, valproate, topiramate, digoxin, and CYP2D6 substrates (donepezil and galantamine) when co-administered with UZEDY [see Clinical Pharmacology (12.3)].

8 USE IN SPECIFIC POPULATIONS

8.1 Pregnancy

Pregnancy Exposure Registry

There is a pregnancy exposure registry that monitors pregnancy outcomes in women exposed to atypical antipsychotics, including UZEDY, during pregnancy. Healthcare providers are encouraged to register patients by contacting the National Pregnancy Registry for Atypical Antipsychotics at 1-866-961-2388 or online at http://womensmentalhealth.org/clinical-and-research-programs/pregnancyregistry/.

Risk Summary

Neonates exposed to antipsychotic drugs during the third trimester of pregnancy are at risk for extrapyramidal and/or withdrawal symptoms following delivery (see Clinical Considerations). Overall, available data from published epidemiologic studies of pregnant women exposed to risperidone have not established a drug-associated risk of major birth defects, miscarriage, or adverse maternal or fetal outcomes (see Data). There are risks to the mother associated with untreated schizophrenia or bipolar I disorder and with exposure to antipsychotics, including UZEDY, during pregnancy (see Clinical Considerations).

Oral administration of risperidone to pregnant mice caused cleft palate at doses 3- to 4-times the oral maximum recommended human dose (MRHD) of 16 mg/day with maternal toxicity observed at 4-times MRHD based on mg/m^2 body surface area. Risperidone was not teratogenic in rats or rabbits at doses up to 6-times the oral MRHD based on mg/m^2 body surface area. Increased stillbirths and decreased birth weight occurred after oral risperidone administration to pregnant rats at 1.5-times the oral MRHD based on mg/m^2 body surface area. Learning was impaired in offspring of rats when the dams were dosed at 0.6-times the oral MRHD and offspring mortality increased at doses 0.1- to 3-times the oral MRHD based on mg/m^2 body surface area.

The background risks of major birth defects and miscarriage for the indicated population is unknown. All pregnancies have a background risk of birth defect, loss, or other adverse outcomes. In the U.S. general population, the estimated background risk of major birth defects and miscarriage in clinically recognized pregnancies is 2 to 4% and 15 to 20%, respectively.

Clinical Considerations

Disease-associated maternal and/or embryo/fetal risk

There is a risk to the mother from untreated schizophrenia or bipolar I disorder, including increased risk of relapse, hospitalization, and suicide. Schizophrenia or bipolar I disorder are associated with increased adverse perinatal outcomes, including preterm birth. It is not known if this is a direct result of the illness or other comorbid factors.

Fetal/Neonatal Adverse Reactions

Extrapyramidal and/or withdrawal symptoms, including agitation, hypertonia, hypotonia, tremor, somnolence, respiratory distress, and feeding disorder have been reported in neonates who were exposed to antipsychotic drugs, including risperidone, during the third trimester of pregnancy. These symptoms have varied in severity. Monitor neonates for extrapyramidal and/or withdrawal symptoms and manage symptoms appropriately. Some neonates recovered within hours or days without specific treatment; others required prolonged hospitalization.

Data

Human Data

Published data from observational studies, birth registries, and case reports on the use of atypical antipsychotics during pregnancy do not report a clear association with antipsychotics and major birth defects. A prospective observational study including 6 women treated with risperidone demonstrated placental passage of risperidone. A retrospective cohort study from a Medicaid database of 9258 women exposed to antipsychotics during pregnancy did not indicate an overall increased risk for major birth defects. There was a small increase in the risk of major birth defects (RR = 1.26, 95% CI = 1.02 to 1.56) and of cardiac malformations (RR = 1.26, 95% CI = 0.88 to 1.81) in a subgroup of 1566 women exposed to risperidone during the first trimester of pregnancy; however, there is no mechanism of action to explain the difference in malformation rates.

Animal data

No developmental toxicity studies were conducted with subcutaneous risperidone suspension.

Oral administration of risperidone to pregnant mice during organogenesis caused cleft palate at 10 mg/kg/day which is 3-times the oral MRHD of 16 mg/day based on mg/m^2 body surface area; maternal toxicity occurred at 4-times the oral MRHD. Risperidone was not teratogenic when administered orally to rats at 0.6 to 10 mg/kg/day and rabbits at 0.3 to 5 mg/kg/day, which are up to 6-times the oral MRHD of 16 mg/day risperidone based on mg/m^2 body surface area. Learning was impaired in offspring of rats dosed orally throughout pregnancy at 1 mg/kg/day which is 0.6-times the oral MRHD and neuronal cell death increased in fetal brains of offspring of rats dosed during pregnancy at 1 and 2 mg/kg/day which are 0.6- and 1.2-times the oral MRHD based on mg/m^2 body surface area; postnatal development and growth of the offspring were also delayed.

Rat offspring mortality increased during the first 4 days of lactation when pregnant rats were dosed throughout gestation at 0.16 to 5 mg/kg/day which are 0.1- to 3-times the oral MRHD of 16 mg/day based on mg/m^2 body surface area. It is not known whether these deaths were due to a direct effect on the fetuses or pups or to effects on the dams; a no-effect dose could not be determined. The rate of stillbirths was increased at 2.5 mg/kg or 1.5-times the oral MRHD based on mg/m^2 body surface area.

In a rat cross-fostering study the number of live offspring was decreased, the number of stillbirths increased, and the birth weight was decreased in offspring of drug-treated pregnant rats. In addition, the number of deaths increased by Day 1 among offspring of drug-treated pregnant rats, regardless of whether or not the offspring were cross-fostered. Risperidone also appeared to impair maternal behavior in that offspring body weight gain and survival (from Day 1 to 4 of lactation) were reduced in offspring born to control but reared by drug-treated dams. All of these effects occurred at 5 mg/kg which is 3-times the oral MRHD based on mg/m^2 and the only dose tested in the study.

8.2 Lactation

Risk Summary

Limited data from published literature reports the presence of risperidone and its metabolite, 9-hydroxyrisperidone, in human breast milk at relative infant dose ranging between 2.3 and 4.7% of the maternal weight-adjusted dosage. There are reports of sedation, failure to thrive, jitteriness, and extrapyramidal symptoms (tremors and abnormal muscle movements) in breastfed infants exposed to risperidone (see Clinical Considerations).

There is no information on the effects of risperidone on milk production. The developmental and health benefits of breastfeeding should be considered along with the mother’s clinical need for UZEDY and any potential adverse effects on the breastfed child from UZEDY or from the mother’s underlying condition.

Clinical Considerations

Infants exposed to UZEDY through breastmilk should be monitored for excess sedation, failure to thrive, jitteriness, and extrapyramidal symptoms (tremors and abnormal muscle movements).

8.3 Females and Males of Reproductive Potential

Infertility

Females

Based on the pharmacologic action of risperidone (D2 receptor antagonism), treatment with UZEDY may result in an increase in serum prolactin levels, which may lead to a reversible reduction in fertility in females of reproductive potential [see Warnings and Precautions (5.6)].

8.4 Pediatric Use

The safety and effectiveness of UZEDY have not been established in pediatric patients.

Juvenile Animal Toxicity Data

No juvenile animal studies were conducted with subcutaneous risperidone suspension.

Juvenile dogs were treated with oral risperidone from weeks 10 to 50 of age (equivalent to the period of childhood through adolescence in humans), at doses of 0.31, 1.25, or 5 mg/kg/day. Bone length and density were decreased with a no-effect dose of 0.31 mg/kg/day; this dose produced plasma AUC of risperidone plus its active metabolite paliperidone (9-hydroxyrisperidone) that were similar to those in children and adolescents receiving the oral MRHD of 6 mg/day. In addition, sexual maturation was delayed at all doses in both males and females. The above effects showed little or no reversibility in females after a 12 week drug-free recovery period.

Juvenile rats, treated with oral risperidone from days 12 to 50 of age (equivalent to the period of infancy through adolescence in humans) showed impaired learning and memory performance (reversible only in females), with a no-effect dose of 0.63 mg/kg/day which is 0.5 times the oral MRHD of 6 mg/day for children, based on mg/m^2 body surface area. This dose produced plasma AUC of risperidone plus paliperidone about half the exposure observed in humans at the oral MRHD. No other consistent effects on neurobehavioral or reproductive development were seen up to the highest tested dose of 1.25 mg/kg/day which is 1 time the oral MRHD and produced plasma AUC of risperidone plus paliperidone that were about two thirds of those observed in humans at the oral MRHD of 6 mg/day for children.

8.5 Geriatric Use

Clinical studies of UZEDY in the treatment of schizophrenia did not include patients older than 65 years to determine whether or not they respond differently from younger patients.

In general, dose selection for geriatric patients should be cautious, usually starting at the low end of the dosing range, reflecting the greater frequency of decreased hepatic, renal, or cardiac function, and of concomitant disease or other drug therapy.

UZEDY is substantially excreted by the kidneys, and the risk of reactions may be greater in patients with impaired renal function. Because geriatric patients are more likely to have decreased renal function, care should be taken in dose selection, and it may be useful to monitor renal function [see Warnings and Precautions (5.7) and Clinical Pharmacology (12.3)].

Elderly patients with dementia-related psychosis treated with UZEDY are at an increased risk of death compared to placebo. UZEDY is not approved for the treatment of patients with dementia‑related psychosis [see Boxed Warning and Warnings and Precautions (5.1, 5.2)].

8.6 Renal Impairment

In patients with renal impairment, titrate with oral risperidone (up to at least 2 mg daily) before initiating treatment with UZEDY [see Dosage and Administration (2.5) and Clinical Pharmacology (12.3)].

UZEDY was not studied in patients with renal impairment.

8.7 Hepatic Impairment

In patients with hepatic impairment, titrate with oral risperidone (up to at least 2 mg daily) before initiating treatment with UZEDY [see Dosage and Administration (2.5) and Clinical Pharmacology (12.3)].

UZEDY has not been studied in patients with hepatic impairment; however, such effect has been investigated with oral risperidone.

8.8 Patients with Parkinson's Disease or Dementia with Lewy Bodies

Patients with Parkinson’s disease or dementia with Lewy bodies can experience increased sensitivity to UZEDY. Manifestations can include confusion, obtundation, postural instability with frequent falls, extrapyramidal symptoms, and clinical features consistent with neuroleptic malignant syndrome.

10 OVERDOSAGE

Human Experience

No cases of overdose were reported in premarketing studies with UZEDY.

In premarketing experience with oral risperidone, there were eight reports of acute risperidone overdosage with estimated doses ranging from 20 to 300 mg and no fatalities. In general, reported signs and symptoms were those resulting from an exaggeration of the drug's known pharmacological effects, i.e., drowsiness and sedation, tachycardia and hypotension, and extrapyramidal symptoms. One case, involving an estimated overdose of 240 mg, was associated with hyponatremia, hypokalemia, prolonged QT, and widened QRS. Another case, involving an estimated overdose of 36 mg, was associated with a seizure.

Postmarketing experience with oral risperidone included reports of acute overdosage with estimated doses of up to 360 mg. In general, the most frequently reported signs and symptoms are those resulting from an exaggeration of the drug's known pharmacological effects, i.e., drowsiness, sedation, tachycardia, hypotension, and extrapyramidal symptoms. Other postmarketing adverse reactions related to oral risperidone overdose include prolonged QT interval and convulsions. Torsade de pointes has been reported in association with combined overdose of oral risperidone and paroxetine.

Management of Overdosage

There is no specific antidote to risperidone. Provide supportive care including close medical supervision and monitoring. Treatment should consist of general measures employed in the management of overdosage with any drug. Consider the possibility of multiple drug overdosage. Ensure an adequate airway, oxygenation, and ventilation. Monitor cardiac rhythm and vital signs.

Consider contacting the Poison Help Line (1-800-222-1222) or medical toxicologist for additional overdosage management recommendations.

11 DESCRIPTION

UZEDY contains risperidone, an atypical antipsychotic. Risperidone belongs to the chemical class of benzisoxazole derivatives. The chemical designation is 3-[2-[4-(6-fluoro-1,2-benzoxazol-3-yl) piperidin-1yl] ethyl]-2-methyl-6,7,8,9-tetrahydropyrido[1,2-a] pyrimidin-4-one. Its molecular formula is C23H27FN4O2 and its molecular weight is 410.5 g/mol.

The structural formula is:

Risperidone is a white to off-white powder. It is practically insoluble in water and soluble in methanol and 0.1 N HCl. It has the following pKa values: 8.28 (piperidine moiety) and 3.12 (pyrimidine moiety).

UZEDY (risperidone) extended-release injectable suspension, for subcutaneous use, is a sterile, preservative free, white to off-white opaque viscous suspension. It is available in the following strengths (and deliverable volumes from a single-dose prefilled syringe): 50 mg (0.14 mL), 75 mg (0.21 mL), 100 mg (0.28 mL), 125 mg (0.35 mL), 150 mg (0.42 mL), 200 mg (0.56 mL), and 250 mg (0.7 mL). The inactive ingredients include dimethyl sulfoxide (45% w/w), methoxy-poly(ethylene glycol)-co-poly(D,L-lactide) (15% w/w), and poly(D,L-lactide)-co-poly(ethylene glycol)-co-poly(D,L-lactide) (10% w/w).

12 CLINICAL PHARMACOLOGY

12.1 Mechanism of Action

The mechanism of action of risperidone, for the listed indications, is unclear. The drug’s therapeutic activity could be mediated through a combination of dopamine Type 2 (D2) and serotonin Type 2 (5HT2) receptor antagonism. The clinical effect from risperidone results from the combined concentrations of risperidone and its major metabolite, 9-hydroxyrisperidone (paliperidone) [see Clinical Pharmacology (12.3)]. Antagonism at receptors other than D2 and 5HT2 may explain some of the other effects of risperidone.

12.2 Pharmacodynamics

Risperidone is a monoaminergic antagonist with high affinity (Ki of 0.12 to 7.3 nM) for the serotonin Type 2 (5HT2), dopamine Type 2 (D2), α1 and α2 adrenergic, and H1 histaminergic receptors. Risperidone showed low to moderate affinity (Ki of 47 to 253 nM) for the serotonin 5HT1C, 5HT1D, and 5HT1A receptors, weak affinity (Ki of 620 to 800 nM) for the dopamine D1 and haloperidol-sensitive sigma site, and no affinity (when tested at concentrations >10^-5 M) for cholinergic muscarinic or β1 and β2 adrenergic receptors.

12.3 Pharmacokinetics

The pharmacokinetics of the risperidone and 9-hydroxyrisperidone combined and the individual components (risperidone and 9-hydroxyrisperidone), following subcutaneous injection of UZEDY, were evaluated in both healthy subjects (n = 53) and in patients with clinically stable schizophrenia and schizoaffective disorder after single doses (12.5 to 225 mg, n = 195) and 3 repeated monthly doses (75 mg and 150 mg, n=24).

For all doses, steady-state levels of risperidone and 9-hydroxyrisperidone were approached within 2 months of UZEDY initiation. Steady-state plasma exposure values of risperidone, 9-hydroxyrisperidone, and risperidone and 9-hydroxyrisperidone combined following once monthly administration of UZEDY are approximately 2- to 2.5-fold higher than single dose exposure, while the values for UZEDY administered once every 2 months are about 1.5-fold higher than the respective single dose exposure. After administration of UZEDY, plasma levels of risperidone, 9-hydroxyrisperidone, and risperidone and 9-hydroxyrisperidone combined (AUC0-tau and Cmax) increase in a dose-proportional manner.

The average exposure values (Cavg,ss) over the dosing period are comparable for UZEDY administered once monthly and once every 2 months at corresponding doses. Following both once monthly (50 mg to 125 mg) and once every 2 months dosing (100 mg to 250 mg), the mean exposure of risperidone and 9-hydroxyrisperidone combined (AUC0-tau) of UZEDY corresponds to that of oral risperidone (2 mg to 5 mg/day) administered over an equivalent dosing period (see Table 1).

No clinically significant difference in the steady state pharmacokinetic exposure of risperidone total active moiety (risperidone and 9-hydroxyrisperidone) following administration of UZEDY 50, 75, and 100 mg once monthly and another risperidone long-acting injection administered as 25, 37.5, and 50 mg once every 2 weeks.

Absorption

UZEDY contains risperidone in a liquid delivery system. Following subcutaneous injection, a depot forms which provides a sustained plasma levels of risperidone and 9-hydroxyrisperidone combined over one month or two months. All UZEDY doses, administered once monthly or once every 2 months, showed two absorption peaks for risperidone in plasma. After subcutaneous administration, median tmax for the risperidone and 9-hydroxyrisperidone combined ranges from 8 to 14 days. Therapeutic concentrations in plasma are within 6 to 24 hours following the first subcutaneous injection.

UZEDY administered in the abdomen and upper arm results in similar pharmacokinetic profiles for all UZEDY doses, permitting either injection site to be used interchangeably.

Distribution

Once absorbed, risperidone is rapidly distributed. The volume of distribution is 1 to 2 L/kg. Risperidone is bound to albumin and α1-acid glycoprotein. The plasma protein binding of risperidone is approximately 90%, and that of its major metabolite, 9-hydroxyrisperidone, is 77%. Neither risperidone nor 9-hydroxyrisperidone displace each other from plasma binding sites.

Elimination

The combined clearance of the risperidone and 9-hydroxyrisperidone following UZEDY administration is 14.3 L/h at steady state. The mean apparent half-life (t1/2) of UZEDY ranges between 14 to 22 days for risperidone, 9-hydroxyrisperidone, and risperidone and 9-hydroxyrisperidone combined.

Metabolism

Risperidone is extensively metabolized in the liver. The main metabolic pathway is through hydroxylation of risperidone to 9-hydroxyrisperidone by the enzyme cytochrome CYP2D6 with minor contribution by CYP3A4. A minor metabolic pathway is through N-dealkylation. The main metabolite, 9-hydroxyrisperidone, has similar pharmacological activity as risperidone. Consequently, the clinical effect of the drug results from the combined concentrations of risperidone plus 9-hydroxyrisperidone).

CYP2D6 is the enzyme responsible for metabolism of many neuroleptics, antidepressants, antiarrhythmics, and other drugs. CYP2D6 is subject to genetic polymorphism (about 6 to 8% of Caucasians, and a very low percentage of Asians, have little or no activity and are “poor metabolizers”) and to inhibition by a variety of substrates and some non-substrates, notably quinidine. Extensive CYP2D6 metabolizers convert risperidone rapidly into 9-hydroxyrisperidone; whereas, poor CYP2D6 metabolizers convert it much more slowly.

Population PK analysis demonstrates that plasma exposure to risperidone and 9-hydroxyrisperidone combined was similar in CYP2D6 extensive, intermediate, poor and non-poor metabolizers following subcutaneous injection with UZEDY.

Excretion

Risperidone and its metabolites are eliminated via the urine and, to a much lesser extent, via the feces. As illustrated by a mass balance study of a single 1 mg oral dose of ^14C-risperidone administered as a solution to three healthy male volunteers, total recovery of radioactivity at 1-week was 84%, including 70% in the urine and 14% in the feces.

Specific Populations

Based on population pharmacokinetic analyses, age, sex, race and weight do not have a clinically meaningful effect on the pharmacokinetics of UZEDY.

Patients with Renal Impairment

UZEDY was not studied in patients with renal impairment; however, such effect has been investigated with oral risperidone. In patients with moderate to severe renal disease treated with oral risperidone, the apparent clearance (CL/F) of risperidone and 9-hydroxyrisperidone combined was decreased by 60% in patients with moderate to severe renal disease compared with young healthy subjects [see Use in Specific Populations (8.6)].

Patients with Hepatic Impairment

The effect of hepatic impairment on the pharmacokinetics of UZEDY has not been studied.

The effect of hepatic impairment on the pharmacokinetics of oral risperidone has been evaluated in a phase I study. While the pharmacokinetics of risperidone in subjects with liver disease were comparable to those in young healthy subjects, the mean free fraction of risperidone in plasma was increased by about 35% because of the diminished concentration of both albumin and α1-acid glycoprotein [see Use in Specific Populations (8.7)].

Geriatric Patients

The pharmacokinetics of UZEDY in geriatric patients has not been studied.

In an open-label trial, steady-state concentrations of risperidone plus 9-hydroxyrisperidone in otherwise healthy elderly patients (≥ 65 years old) treated with another risperidone long-acting injection, given once every 2 weeks, for up to 12 months fell within the range of values observed in otherwise healthy nonelderly patients.

Drug Interaction Studies

No specific drug interaction studies have been performed with UZEDY. The drug interaction data provided in this section is based on studies with oral risperidone. Effects of other drugs on the exposures of risperidone, 9-hydroxyrisperidone, and risperidone and 9-hydroxyrisperidone combined as well as the effects of risperidone on the exposures of other drugs is summarized below.

Effects of Other Drugs on Risperidone, 9-hydroxyrisperidone, and Risperidone and 9-hydroxyrisperidone Combined Pharmacokinetics

Strong CYP2D6 Inhibitors (Fluoxetine and Paroxetine)

Fluoxetine (20 mg once daily) and paroxetine (20 mg once daily), potent CYP2D6 inhibitors, have been shown to increase the plasma concentration of risperidone by 2.5- to 2.8-fold and 3- to 9-fold, respectively. Fluoxetine did not affect the plasma concentration of 9-hydroxyrisperidone. Paroxetine lowered the concentration of 9-hydroxyrisperidone by about 10%. The effects of discontinuation of concomitant fluoxetine or paroxetine therapy on the pharmacokinetics of risperidone and 9-hydroxyrisperidone have not been studied.

Moderate CYP3A4 Inhibitor (Erythromycin)

There were no significant interactions between oral risperidone and erythromycin, a moderate CYP3A4 inhibitor.

Strong CYP3A4 Inducer (Carbamazepine)

Carbamazepine co-administration with oral risperidone decreased the steady-state plasma concentrations of risperidone and 9-hydroxyrisperidone by about 50%. Plasma concentrations of carbamazepine did not appear to be affected. Co-administration of other known CYP3A4 enzyme inducers (e.g., phenytoin, rifampin, and phenobarbital) with risperidone may cause similar decreases in the combined plasma concentrations of risperidone and 9-hydroxyrisperidone, which could lead to decreased efficacy of UZEDY treatment.

Amitriptyline, Cimetidine, Ranitidine, Clozapine

Clinically meaningful pharmacokinetic interaction between UZEDY and other drugs, such as amitriptyline, cimetidine, ranitidine, and clozapine, is not expected.

- Amitriptyline did not affect the pharmacokinetics of risperidone or of risperidone and 9-hydroxyrisperidone combined following concomitant administration with oral risperidone.
- Cimetidine and ranitidine increased the bioavailability of oral risperidone by 64% and 26%, respectively. However, cimetidine did not affect the AUC of risperidone and 9-hydroxyrisperidone combined, whereas ranitidine increased the AUC of risperidone and 9-hydroxyrisperidone combined by 20%.
- Chronic administration of clozapine with oral risperidone have shown to affect the clearance of risperidone; however, clinical relevance is unknown.
- There was no clinically relevant effect of oral risperidone (1 to 6 mg/day) on the pharmacokinetics of topiramate 400 mg/day.

Effects of Oral Risperidone on Pharmacokinetics of Other Drugs

Lithium

Repeated doses of oral risperidone (3 mg twice daily) did not affect the exposure (AUC) or peak plasma concentrations (Cmax) of lithium (n = 13).

Valproate

Repeated doses of oral risperidone (4 mg once daily) did not affect the predose or average plasma concentrations and exposure (AUC) of valproate (1000 mg/day in three divided doses) compared to placebo (n = 21). However, there was a 20% increase in valproate peak plasma concentration (Cmax) after concomitant administration of oral risperidone.

Topiramate

Oral risperidone administered at doses from 1 to 6 mg/day concomitantly with topiramate 400 mg/day resulted in a 23% decrease in risperidone Cmax and a 33% decrease in risperidone AUC0‑12 hour at steady state. Minimal reductions in the exposure to risperidone and 9-hydroxyrisperidone combined, and no change for 9-hydroxyrisperidone were observed. This interaction is unlikely to be of clinical significance. There was no clinically relevant effect of oral risperidone on the pharmacokinetics of topiramate.

Digoxin

Oral risperidone (0.25 mg twice daily) did not show a clinically relevant effect on the pharmacokinetics of digoxin.

CYP2D6 Substrates

In vitro studies indicate that risperidone is a relatively weak inhibitor of CYP2D6. Therefore, UZEDY is not expected to substantially inhibit the clearance of drugs that are metabolized by this enzymatic pathway. In drug interaction studies, oral risperidone did not significantly affect the pharmacokinetics of donepezil and galantamine, which are metabolized by CYP2D6.

13 NONCLINICAL TOXICOLOGY

13.1 Carcinogenesis, Mutagenesis, Impairment of Fertility

Carcinogenesis

No carcinogenicity studies were conducted with subcutaneous risperidone suspension. Carcinogenicity studies were conducted with oral risperidone in mice and rats. Risperidone was administered in the diet at doses of 0.63, 2.5, and 10 mg/kg for 18-months to mice and for 25-months to rats. These doses are equivalent to approximately 0.2-, 0.75-, and 3-times (mice) and 0.4-, 1.5-, and 6-times (rats) the oral MRHD of 16 mg/day, based on a mg/m^2 body surface area. A maximum tolerated dose was not achieved in male mice. There were statistically significant increases in pituitary gland adenomas, endocrine pancreas adenomas, and mammary gland adenocarcinomas. The table below summarizes the multiples of the human dose on a mg/m^2 (mg/kg) basis at which these tumors occurred.

Table 14: Summary of Tumor Occurrence at the Multiples of the Human Oral Dose on a mg/m^2 (mg/kg) Basis with Oral Risperidone Dosing
Tumor Type | Species | Sex | Multiples of Maximum Human Dose in mg/m^2 (mg/kg)
Tumor Type | Species | Sex | Lowest Effect Level | Highest No-Effect Level
Pituitary adenomas | mouse | Female | 0.75 (9.4) | 0.2 (2.4)
Endocrine pancreas; adenomas | rat | Male | 1.5 (9.4) | 0.4 (2.4)
Mammary gland; adenocarcinomas | mouse | Female | 0.2 (2.4) | none
 | rat | Female | 0.4 (2.4) | none
 | rat | Male | 6.0 (37.5) | 1.5 (9.4)
Mammary gland; neoplasm, Total | rat | Male | 1.5 (9.4) | 0.4 (2.4)

Antipsychotic drugs have been shown to chronically elevate prolactin levels in rodents. Serum prolactin levels were not measured during the risperidone carcinogenicity studies; however, measurements during subchronic toxicity studies showed that risperidone elevated serum prolactin levels 5- to 6-fold in mice and rats at the same doses used in the carcinogenicity studies. An increase in mammary, pituitary, and endocrine pancreas neoplasms has been found in rodents after chronic administration of other antipsychotic drugs and is considered to be prolactin-mediated. The relevance for human risk of the findings of prolactin-mediated endocrine tumors in rodents is unclear [see Warnings and Precautions (5.6)].

Mutagenesis

No evidence of mutagenic or clastogenic potential for risperidone was found in the in vitro tests of Ames gene mutation, the mouse lymphoma assay, rat hepatocyte DNA-repair assay, the chromosomal aberration test in human lymphocytes, Chinese hamster ovary cells, or in the in vivo oral micronucleus test in mice and the sex-linked recessive lethal test in Drosophila.

No evidence of mutagenic potential was found in the in vitro Ames reverse mutation test for the copolymer mixture of methoxy-poly(ethylene glycol)-co-poly(D,L-lactide) and poly(D,L-lactide)-co-poly(ethylene glycol)-co-poly(D,L-lactide) dissolved in dimethyl sulfoxide.

Impairment of Fertility

No mating and fertility studies were conducted with subcutaneous risperidone suspension. Oral risperidone (0.16 to 5 mg/kg) impaired mating, but not fertility, in rat reproductive studies at doses 0.1- to 3-times the oral MRHD, of 16 mg/day based on mg/m^2 body surface area. The effect appeared to be in females, since impaired mating behavior was not noted in the male fertility study. In a subchronic study in Beagle dogs in which risperidone was administered orally at doses of 0.31 to 5 mg/kg, sperm motility and concentration were decreased at doses 0.6- to 10-times the oral MRHD based on mg/m^2 body surface area. Dose-related decreases were also noted in serum testosterone at the same doses. Serum testosterone and sperm parameters partially recovered, but remained decreased after treatment was discontinued. A no-effect dose could not be determined in either rat or dog.

14 CLINICAL STUDIES

14.1 Schizophrenia

The efficacy of UZEDY for the treatment of schizophrenia in adults is based, in part, on the established effectiveness of oral risperidone as well as in a randomized withdrawal study (Study 1: NCT03503318) with UZEDY in adults who met the DSM-5 criteria for schizophrenia. The results from Study 1 are presented below.

Study 1 was a randomized withdrawal study in patients with schizophrenia consisting of a 12-week open-label oral risperidone (2 mg to 5 mg) stabilization phase, followed by a placebo-controlled phase in which patients were randomized to UZEDY (once monthly or once every 2 months) or placebo for a variable time until impending relapse or study completion.

UZEDY was administered once monthly or once every 2 months at doses of 50 mg to 250 mg compared with monthly placebo injections in adult patients meeting DSM-5 criteria for schizophrenia. Patients were required to have a Positive and Negative Syndrome Scale (PANSS) total score lower than 100 at the screening visit. Eligible screened patients were enrolled into an oral conversion and stabilization stage (12 weeks). Patients were administered oral risperidone (2 mg to 5 mg per day) to establish stability and tolerability. Eligible patients were randomized into the double-blind period of the study if they met the following randomization criteria for at least 4 consecutive weeks prior to the baseline visit: outpatient status, PANSS total ≤80, Minimal presence of specific psychotic symptoms on the PANSS, as measured by a score of ≤4 on each of the following items: conceptual disorganization, suspiciousness, hallucinatory behavior, and unusual thought content [CGI-S score ≤4 (moderately ill); CGI-SS score ≤2 (mildly suicidal) on Part 1 and ≤5 (minimally worsened) on Part 2].

In the double-blind stage (variable in duration), patients were randomized to receive placebo, once monthly UZEDY, or once every 2 months UZEDY in doses based on the oral dose on which they were previously stabilized in the oral conversion and stabilization stage.

The primary efficacy endpoint was time to impending relapse. Relapse was defined as one or more of the following items:

- Clinical Global Impression–Improvement (CGI-I) of ≥5 (greater than or equal to minimally worse, i.e., minimally worse, much worse or very much worse), AND

- an increase of any of the following individual Positive and Negative Syndrome Scale (PANSS) items: conceptual disorganization, hallucinatory behavior, suspiciousness, and unusual thought content, to a score of >4 with an absolute increase of ≥2 on that specific item since randomization, OR
- an increase in any of the following 4 individual PANSS items: conceptual disorganization, hallucinatory behavior, suspiciousness, and unusual thought content, to a score of >4 and an absolute increase of ≥4 on the combined score of these 4 PANSS items (conceptual disorganization, hallucinatory behavior, suspiciousness, and unusual thought content) since randomization

- hospitalization due to worsening of psychotic symptoms (including partial hospitalization programs), excluding hospitalization for psychosocial reasons
- Clinical Global Impression-Severity of Suicidality (CGI-SS) of 4 (severely suicidal) or 5 (attempted suicide) on Part 1 and/or 6 (much worse) or 7 (very much worse) on Part 2
- violent behavior resulting in clinically significant self-injury, injury to another person, or property damage

The mean baseline PANSS total score was similar across the groups (approximately 61 in each group). Most patients were male (61% per group) and the median age was 52 years. Most patients in this study were black or African American (57% to 61% per group). Of the 544 patients randomized to treatment, 543 were included in the intent-to-treat (ITT) population.

The study met its prespecified primary endpoint for both the UZEDY once monthly and once every 2 months dosing regimens. Time to relapse was statistically significantly longer in the UZEDY-treated groups compared to the placebo group. The cumulative percentage of relapse over time was calculated using Kaplan-Meier product limit estimate of the time to relapse during the randomized withdrawal trial as shown in Figure 1.

Subgroup analyses by gender, age, and race did not suggest any clear evidence of differential responsiveness to UZEDY.

Figure 1: Kaplan-Meier Curve of Cumulative Proportion of UZEDY-Treated Patients with Relapse Over Time

14.2 Bipolar Disorder - Monotherapy

UZEDY is to be administered subcutaneously. The efficacy of UZEDY for the treatment of bipolar disorder monotherapy in adults is based on the established effectiveness of another risperidone long-acting injection, given once every 2 weeks, that was administered intramuscularly.

The efficacy of risperidone long-acting injection for the maintenance treatment of bipolar I disorder was established in a multicenter, double-blind, placebo-controlled study of adult patients who met DSM-IV criteria for Bipolar Disorder Type I, who were stable on medications or experiencing an acute manic or mixed episode. The results of the adequate and well-controlled study are presented below.

A total of 501 patients were treated during a 26-week open-label period with another risperidone long-acting injection (starting dose of 25 mg, and titrated, if deemed clinically desirable, to 37.5 mg or 50 mg; in patients not tolerating the 25 mg dose, the dose could be reduced to 12.5 mg), given once every 2 weeks. In the open-label phase, 303 (60%) patients were judged to be stable and were randomized to double-blind treatment with either the same dose of another risperidone long-acting injection, given once every 2 weeks, or placebo and monitored for relapse. The primary endpoint was time to relapse to any mood episode (depression, mania, hypomania, or mixed).

Time to relapse was delayed in patients receiving another risperidone long-acting injection, given once every 2 weeks, monotherapy compared with patients receiving placebo. The majority of relapses were due to manic rather than depressive symptoms. Based on their bipolar disorder history, subjects entering this study had, on average, more manic episodes than depressive episodes.

14.3 Bipolar Disorder - Adjunctive Therapy

UZEDY is to be administered subcutaneously. The efficacy of UZEDY for the treatment of bipolar disorder as adjunctive therapy in adults is based on the established effectiveness of another risperidone long-acting injection, given once every 2 weeks, that was administered intramuscularly.

The efficacy of risperidone long-acting injection as an adjunct to treatment with lithium or valproate for the maintenance treatment of bipolar I disorder was established in a multi-center, randomized, double-blind, placebo-controlled study of adult patients who met DSM-IV criteria for Bipolar Disorder Type I and who experienced at least 4 episodes of mood disorder requiring psychiatric/clinical intervention in the previous 12 months, including at least 2 episodes in the 6 months prior to the start of the study. The results of the adequate and well-controlled study are presented below.

A total of 240 patients were treated during a 16-week open-label period with another risperidone long-acting injection (starting dose of 25 mg, and titrated, if deemed clinically desirable, to 37.5 mg or 50 mg), given once every 2 weeks, as adjunctive therapy in addition to continuing their usual treatment for bipolar disorder, which consisted of mood stabilizers (primarily lithium and valproate), antidepressants, and/or anxiolytics. All oral antipsychotics were discontinued after the first three weeks after the initial injection of risperidone long-acting injection. In the open-label phase, 124 (51.7%) were judged to be stable for at least the last 4 weeks and were randomized to double-blind treatment with either the same dose of another risperidone long-acting injection, given once every 2 weeks, or placebo in addition to continuing their usual treatment and monitored for relapse during a 52-week period. The primary endpoint was time to relapse to any new mood episode (depression, mania, hypomania, or mixed).

Time to relapse was delayed in patients receiving adjunctive therapy with another risperidone long-acting injection, given once every 2 weeks, compared with patients receiving adjunctive therapy with placebo. The relapse types were about half depressive and half manic or mixed episodes.

16 HOW SUPPLIED/STORAGE AND HANDLING

How Supplied

UZEDY (risperidone) extended-release injectable suspension, for subcutaneous use, is a sterile, preservative free, white to off-white opaque viscous suspension.

UZEDY is supplied in single-dose kits as follows:

- 50 mg/0.14 mL single-dose prefilled syringe, packaged in a carton with one 21 gauge, 5/8-inch needle (NDC 51759-305-10)
- 75 mg/0.21 mL single-dose prefilled syringe, packaged in a carton with one 21 gauge, 5/8-inch needle (NDC 51759-410-10)
- 100 mg/0.28 mL single-dose prefilled syringe, packaged in a carton with one 21 gauge, 5/8-inch needle (NDC 51759-520-10)
- 125 mg/0.35 mL single-dose prefilled syringe, packaged in a carton with one 21 gauge, 5/8-inch needle (NDC 51759-630-10)
- 150 mg/0.42 mL single-dose prefilled syringe, packaged in a carton with one 21 gauge, 5/8-inch needle (NDC 51759-740-10)
- 200 mg/0.56 mL single-dose prefilled syringe, packaged in a carton with one 21 gauge, 5/8-inch needle (NDC 51759-850-10)
- 250 mg/0.7 mL single-dose prefilled syringe, packaged in a carton with one 21 gauge, 5/8-inch needle (NDC 51759-960-10)

The prefilled syringe cap is not made with natural rubber latex.

Storage and Handling

Store in refrigerator at 2°C to 8°C (36°F to 46°F) in the original carton to protect from light.

UZEDY may be stored in unopened original packaging at room temperature, 20°C to 25°C (68°F to 77°F), for up to 90 days. If unopened, UZEDY may be returned to refrigerated storage within 90 days. Once the carton is opened, administer UZEDY or discard.

17 PATIENT COUNSELING INFORMATION

Neuroleptic Malignant Syndrome (NMS)

Counsel patients about a potentially fatal adverse reaction, Neuroleptic Malignant Syndrome (NMS) that has been reported in association with administration of antipsychotic drugs. Advise patients, family members, or caregivers to contact the healthcare provider or report to the emergency room if they experience signs and symptoms of NMS [see Warnings and Precautions (5.3)].

Tardive Dyskinesia

Counsel patients on the signs and symptoms of tardive dyskinesia and to contact their healthcare provider if these abnormal movements occur [see Warnings and Precautions (5.4)].

Metabolic Changes

Educate patients about the risk of metabolic changes, how to recognize symptoms of hyperglycemia and diabetes mellitus and the need for specific monitoring, including blood glucose, lipids, and weight [see Warnings and Precautions (5.5)].

Hyperprolactinemia

Counsel patients on signs and symptoms of hyperprolactinemia that may be associated with chronic use of UZEDY. Advise them to seek medical attention if they experience any of the following: amenorrhea or galactorrhea in females, erectile dysfunction, or gynecomastia in males [see Warnings and Precautions (5.6)].

Orthostatic Hypotension and Syncope

Educate patients about the risk of orthostatic hypotension and syncope, particularly at the time of initiating treatment, re-initiating treatment or increasing the dose [see Warnings and Precautions (5.7)].

Leukopenia/Neutropenia

Advise patients with a pre-existing low WBC or a history of drug-induced leukopenia/neutropenia that they should have their CBC monitored while being treated with UZEDY [see Warnings and Precautions (5.9)].

Potential for Cognitive and Motor Impairment

Inform patients that UZEDY has the potential to impair judgement, thinking, and motor skills. Caution patients about performing activities requiring mental alertness, such as operating hazardous machinery, or operating a motor vehicle, until they are reasonably certain that UZEDY therapy does not affect them adversely [see Warnings and Precautions (5.10)].

Priapism

Advise patients of the possibility of painful or prolonged penile erections (priapism). Instruct the patient to seek immediate medical attention in the event of priapism [see Warnings and Precautions (5.13)].

Heat Exposure and Dehydration

Educate patients regarding appropriate care in avoiding overheating and dehydration [see Warnings and Precautions (5.14)].

Concomitant Medication

Advise patients to inform their healthcare providers if they are taking, or plan to take, any prescription or over-the-counter drugs, as there is a potential for interaction [see Drug Interactions (7)].

Alcohol

Advise patients to avoid alcohol during treatment with UZEDY [see Drug Interactions (7.1)].

Pregnancy

Advise patients to notify their healthcare professional if they become pregnant or intend to become pregnant during treatment with UZEDY. Advise patients that UZEDY may cause extrapyramidal and/or withdrawal symptoms (agitation, hypertonia, hypotonia, tremor, somnolence, respiratory distress, and feeding disorder) in a neonate. Advise patients that there is a pregnancy registry that monitors pregnancy outcomes in women exposed to UZEDY during pregnancy [see Use in Specific Populations (8.1)].

Lactation

Advise breastfeeding women using UZEDY to monitor infants for somnolence, failure to thrive, jitteriness, and extrapyramidal symptoms (tremors and abnormal muscle movements) and to seek medical care if they notice these signs [see Use in Specific Populations (8.2)].

Infertility

Advise females of reproductive potential that UZEDY may impair fertility due to an increase in serum prolactin levels. The effects on fertility are reversible [see Use in Specific Populations (8.3)].

UZE-005

Manufactured for:
Teva Neuroscience, Inc.
Parsippany, NJ 07054

©2025 Teva Neuroscience, Inc.

Package/Label Display Panel

1 month dosing

For administration by a healthcare professional

Rx Only

UZEDY® (risperiDONE) extended-release injectable suspension

FOR SUBCUTANEOUS USE ONLY

NDC 51759-305-10
One single-dose prefilled syringe
50 mg/0.14 mL administered every one month

Store in refrigerator at 2°C to 8°C (36°F to 46°F) in the original carton to protect from light.

Allow UZEDY to sit in its packaging at room temperature at 20°C to 25°C(68°F to 77°F) for at least 30 minutes prior to administration.

UZEDY may be stored in unopened original packaging at room temperature, 20°C to 25°C (68°F to 77°F), for up to 90 days. If unopened, UZEDY may be returned to refrigerated storage within 90 days.

Once the carton is opened, administer UZEDY or discard.

OPEN HERE
teva

Package/Label Display Panel

1 month dosing

For administration by a healthcare professional

Rx Only

UZEDY® (risperiDONE) extended-release injectable suspension
FOR SUBCUTANEOUS USE ONLY

NDC 51759-410-10
One single-dose prefilled syringe
75 mg/0.21 mL administered every one month

Store in refrigerator at 2°C to 8°C (36°F to 46°F) in the original carton to protect from light.

Allow UZEDY to sit in its packaging at room temperature at 20°C to 25°C(68°F to 77°F) for at least 30 minutes prior to administration.

UZEDY may be stored in unopened original packaging at room temperature, 20°C to 25°C (68°F to 77°F), for up to 90 days. If unopened, UZEDY may be returned to refrigerated storage within 90 days.

Once the carton is opened, administer UZEDY or discard.

OPEN HERE
teva

Package/Label Display Panel

FOR ADMINISTRATION BY A HEALTHCARE PROFESSIONAL

1 month dosing OR 2 month dosing Rx Only

UZEDY® (risperiDONE) extended-release injectable suspension
FOR SUBCUTANEOUS USE ONLY

NDC 51759-520-10
One single-dose prefilled syringe
100 mg/0.28 mL administered every one or two months

Store in refrigerator at 2°C to 8°C (36°F to 46°F) in the original carton to protect from light.

Allow UZEDY to sit in its packaging at room temperature at 20°C to 25°C(68°F to 77°F) for at least 30 minutes prior to administration.

UZEDY may be stored in unopened original packaging at room temperature, 20°C to 25°C (68°F to 77°F), for up to 90 days. If unopened, UZEDY may be returned to refrigerated storage within 90 days.

Once the carton is opened, administer UZEDY or discard.

OPEN HERE
teva

Package/Label Display Panel

1 month dosing

For administration by a healthcare professional

Rx Only

UZEDY® (risperiDONE) extended-release injectable suspension
FOR SUBCUTANEOUS USE ONLY

NDC 51759-630-10
One single-dose prefilled syringe
125 mg/0.35 mL administered every one month

Store in refrigerator at 2°C to 8°C (36°F to 46°F) in the original carton to protect from light.

Allow UZEDY to sit in its packaging at room temperature at 20°C to 25°C(68°F to 77°F) for at least 30 minutes prior to administration.

UZEDY may be stored in unopened original packaging at room temperature, 20°C to 25°C (68°F to 77°F), for up to 90 days. If unopened, UZEDY may be returned to refrigerated storage within 90 days.

Once the carton is opened, administer UZEDY or discard.

OPEN HERE
teva

Package/Label Display Panel

2 month dosing

For administration by a healthcare professional

Rx Only

UZEDY® (risperiDONE) extended-release injectable suspension
FOR SUBCUTANEOUS USE ONLY

NDC 51759-740-10
One single-dose prefilled syringe
150 mg/0.42 mL administered every two months

Store in refrigerator at 2°C to 8°C (36°F to 46°F) in the original carton to protect from light.

Allow UZEDY to sit in its packaging at room temperature at 20°C to 25°C(68°F to 77°F) for at least 30 minutes prior to administration.

UZEDY may be stored in unopened original packaging at room temperature, 20°C to 25°C (68°F to 77°F), for up to 90 days. If unopened, UZEDY may be returned to refrigerated storage within 90 days.

Once the carton is opened, administer UZEDY or discard.

OPEN HERE
teva

Package/Label Display Panel

2 month dosing

For administration by a healthcare professional

Rx Only

UZEDY® (risperiDONE) extended-release injectable suspension
FOR SUBCUTANEOUS USE ONLY

NDC 51759-850-10
One single-dose prefilled syringe
200 mg/0.56 mL administered every two months

Store in refrigerator at 2°C to 8°C (36°F to 46°F) in the original carton to protect from light.

Allow UZEDY to sit in its packaging at room temperature at 20°C to 25°C(68°F to 77°F) for at least 30 minutes prior to administration.

UZEDY may be stored in unopened original packaging at room temperature, 20°C to 25°C (68°F to 77°F), for up to 90 days. If unopened, UZEDY may be returned to refrigerated storage within 90 days.

Once the carton is opened, administer UZEDY or discard.

OPEN HERE
teva

Package/Label Display Panel

2 month dosing

For administration by a healthcare professional

Rx Only

UZEDY® (risperiDONE) extended-release injectable suspension
FOR SUBCUTANEOUS USE ONLY

NDC 51759-960-10
One single-dose prefilled syringe
250 mg/0.7 mL administered every two months

Store in refrigerator at 2°C to 8°C (36°F to 46°F) in the original carton to protect from light.

Allow UZEDY to sit in its packaging at room temperature at 20°C to 25°C(68°F to 77°F) for at least 30 minutes prior to administration.

UZEDY may be stored in unopened original packaging at room temperature, 20°C to 25°C (68°F to 77°F), for up to 90 days. If unopened, UZEDY may be returned to refrigerated storage within 90 days.

Once the carton is opened, administer UZEDY or discard.

OPEN HERE
teva